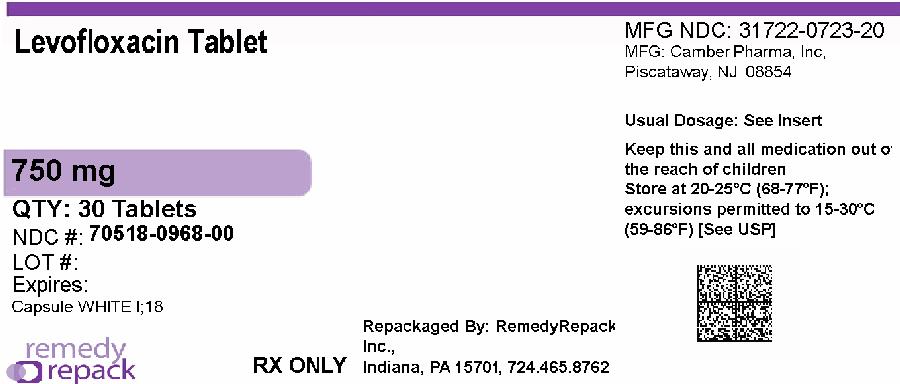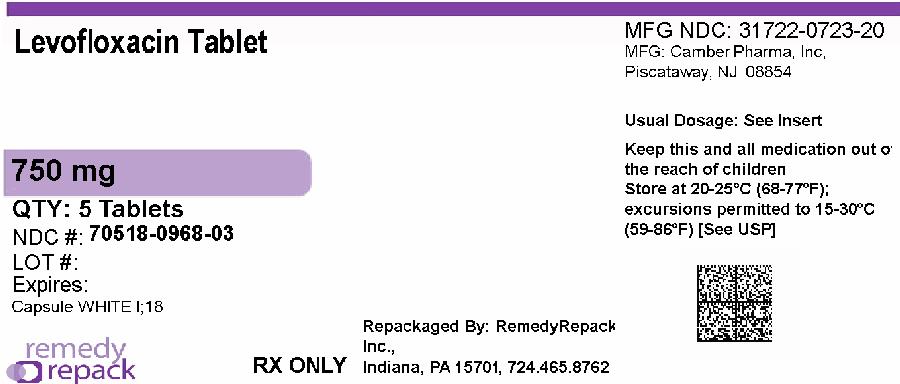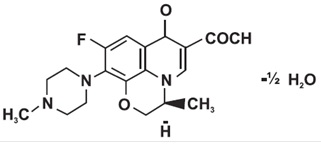 DRUG LABEL: Levofloxacin
NDC: 70518-0968 | Form: TABLET, FILM COATED
Manufacturer: REMEDYREPACK INC.
Category: prescription | Type: HUMAN PRESCRIPTION DRUG LABEL
Date: 20260218

ACTIVE INGREDIENTS: LEVOFLOXACIN 750 mg/1 1
INACTIVE INGREDIENTS: CROSCARMELLOSE SODIUM; HYPROMELLOSES; MAGNESIUM STEARATE; CELLULOSE, MICROCRYSTALLINE; POLYETHYLENE GLYCOL, UNSPECIFIED; POLYSORBATE 80; POVIDONE; TITANIUM DIOXIDE

HIGHLIGHTS OF PRESCRIBING INFORMATION

These highlights do not include all the information needed to use LEVOFLOXACIN TABLETS safely and effectively. See full prescribing information for LEVOFLOXACIN TABLETS.
LEVOFLOXACIN tablets, for oral use
Initial U.S. Approval: 1996

RECENT MAJOR CHANGES

Warnings and Precautions Hypersensitivity Reactions (5.7) 06/2024

WARNING: SERIOUS ADVERSE REACTIONS INCLUDING TENDINITIS, TENDON RUPTURE, PERIPHERAL NEUROPATHY, CENTRAL NERVOUS SYSTEM EFFECTS AND EXACERBATION OF MYASTHENIA GRAVIS

See full prescribing information for complete boxed warning.
Fluoroquinolones, including levofloxacin, have been associated with disabling and potentially irreversible serious adverse reactions that have occurred together (5.1), including:
o Tendinitis and tendon rupture (5.2)
o Peripheral neuropathy (5.3)
o Central nervous system effects (5.4)
Discontinue levofloxacin immediately and avoid the use of fluoroquinolones, including levofloxacin, in patients who experience any of these serious adverse reactions (5.1)
Fluoroquinolones, including levofloxacin, may exacerbate muscle weakness in patients with myasthenia gravis. Avoid levofloxacin in patients with a known history of myasthenia gravis [see Warnings and Precautions (5.5)].
Because fluoroquinolones, including levofloxacin, have been associated with serious adverse reactions (5.1 to 5.15), reserve levofloxacin for use in patients who have no alternative treatment options for the following indications:
o Uncomplicated urinary tract infection (1.12)
o Acute bacterial exacerbation of chronic bronchitis (1.13)
o Acute bacterial sinusitis (1.14)

1 INDICATIONS AND USAGE

Levofloxacin is a fluoroquinolone antibacterial indicated in adults (18 years of age and older) with infections caused by designated, susceptible bacteria and in pediatric patients where indicated (1, 12.4).
• Pneumonia: Nosocomial (1.1) and Community Acquired (1.2, 1.3)
• Skin and Skin Structure Infections (SSSI): Complicated (1.4) and Uncomplicated (1.5)
• Chronic bacterial prostatitis (1.6)
• Inhalational Anthrax, Post-Exposure in adult and pediatric patients (1.7)
• Plague in adult and pediatric patients (1.8)
• Urinary Tract Infections (UTI): Complicated (1.9, 1.10) and Uncomplicated (1.12)
• Acute Pyelonephritis (1.11)
• Acute Bacterial Exacerbation of Chronic Bronchitis (1.13)
• Acute Bacterial Sinusitis (1.14)
Usage
To reduce the development of drug-resistant bacteria and maintain the effectiveness of levofloxacin and other antibacterial drugs, levofloxacin should be used only to treat or prevent infections that are proven or strongly suspected to be caused by bacteria (1.15).

2 DOSAGE AND ADMINISTRATION

• Administer levofloxacin tablets to pediatric patients weighing 30 kg and greater only (2.1, 2.2).
• Levofloxacin tablets cannot be administered to pediatric patients who weigh less than 30 kg because of the limitations of the available strengths. Alternative formulations of levofloxacin may be considered for pediatric patients who weigh less than 30 kg (2.2).

Dosage in Adult and Pediatric Patients with Creatinine Clearance greater than or equal to 50 mL/minute (2.1, 2.2)
Type of Infection | Dose Every 24 hours | Duration (days)
Nosocomial Pneumonia (1.1) | 750 mg | 7 to 14
Community Acquired Pneumonia (1.2) | 500 mg | 7 to 14
Community Acquired Pneumonia (1.3) | 750 mg | 5
Complicated SSSI (1.4) | 750 mg | 7 to 14
Uncomplicated SSSI (1.5) | 500 mg | 7 to 10
Chronic Bacterial Prostatitis (1.6) | 500 mg | 28
Inhalational Anthrax (Post-Exposure) (1.7) Adults and Pediatric Patients 50 kg or greater Pediatric Patients 30 kg to less than 50 kg (2.2) | 500 mg 250 mg every 12 hours | 60 60
Plague (1.8) Adults and Pediatric Patients 50 kg or greater Pediatric Patients 30 kg to less than 50 kg (2.2) | 500 mg 250 mg every 12 hours | 10 to 14 10 to 14
Complicated UTI (1.9) or Acute Pyelonephritis (1.11) | 750 mg | 5
Complicated UTI (1.10) or Acute Pyelonephritis (1.11) | 250 mg | 10
Uncomplicated UTI (1.12) | 250 mg | 3
Acute Bacterial Exacerbation of Chronic Bronchitis (1.13) | 500 mg | 7
Acute Bacterial Sinusitis (1.14) | 750 mg | 5
Acute Bacterial Sinusitis (1.14) | 500 mg | 10 to 14

• Adjust dose for creatinine clearance less than 50 mL/minute (2.3, 8.6, 12.3)

3 DOSAGE FORMS AND STRENGTHS

Tablets: 750 mg

4 CONTRAINDICATIONS

Known hypersensitivity to levofloxacin or other quinolones (4, 5.7)

5 WARNINGS AND PRECAUTIONS

- Anaphylactic reactions and allergic skin reactions, serious, occasionally fatal, may occur after first dose (4, 5.7)
- Hematologic (including agranulocytosis, thrombocytopenia), and renal toxicities may occur after multiple doses (5.6)
- Hepatotoxicity: Severe, and sometimes fatal, hepatotoxicity has been reported. Discontinue immediately if signs and symptoms of hepatitis occur (5.8)
- Clostridium difficile-associated colitis: evaluate if diarrhea occurs (5.10)
- Prolongation of the QT interval and isolated cases of torsade de pointes have been reported. Avoid use in patients with known prolongation, those with hypokalemia, and with other drugs that prolong the QT interval (5.11, 8.5)

6 ADVERSE REACTIONS

The most common reactions (≥3%) were nausea, headache, diarrhea, insomnia, constipation and dizziness (6.2)
To report SUSPECTED ADVERSE REACTIONS, contact Hetero Labs Limited at 1-866-495-1995 or FDA at 1-800-FDA-1088 or www.fda.gov/medwatch.

7 DRUG INTERACTIONS

Interacting Drug | Interaction
Multivalent cation-containing products including antacids, metal cations or didanosine | Absorption of levofloxacin is decreased when the tablets are taken within 2 hours of these products. (2.4, 7.1)
Warfarin | Effect may be enhanced. Monitor prothrombin time, INR and watch for bleeding (7.2)
Antidiabetic agents | Carefully monitor blood glucose (5.13, 7.3)

8 USE IN SPECIFIC POPULATIONS

• Geriatrics:Severe hepatotoxicity has been reported. The majority of reports describe patients 65 years of age or older (5.8, 8.5, 17). May have increased risk of tendinopathy (including rupture), especially with concomitant corticosteroid use (5.2, 8.5, 17). May be more susceptible to prolongation of the QT interval. (5.11, 8.5, 17).
• Pediatrics:Musculoskeletal disorders (arthralgia, arthritis, tendinopathy, and gait abnormality) seen in more levofloxacin-treated patients than in comparator. Shown to cause arthropathy and osteochondrosis in juvenile animals (5.12, 8.4, 13.2). Safety in pediatric patients treated for more than 14 days has not been studied. Risk-benefit appropriate only for the treatment of inhalational anthrax (post-exposure) (1.7, 2.2, 8.4, 14.9) and plague (1.8, 2.2, 8.4, 14.10)
• Lactation:Breastfeeding is not recommended during treatment, but a lactating woman may pump and discard breastmilk during treatment and an additional 2 days after the last dose. In patients treated for inhalational anthrax (post exposure), consider the risks and benefits of continuing breastfeeding.

FULL PRESCRIBING INFORMATION

WARNING: SERIOUS ADVERSE REACTIONS INCLUDING TENDINITIS, TENDON RUPTURE, PERIPHERAL NEUROPATHY, CENTRAL NERVOUS SYSTEM EFFECTS AND EXACERBATION OF MYASTHENIA GRAVIS

• Fluoroquinolones, including levofloxacin, have been associated with disabling and potentially irreversible serious adverse reactions that have occurred together [see Warnings and Precautions (5.1)], including:
o Tendinitis and tendon rupture [see Warnings and Precautions (5.2)]
o Peripheral neuropathy [see Warnings and Precautions (5.3)]
o Central nervous system effects [see Warnings and Precautions (5.4)]
Discontinue levofloxacin immediately and avoid the use of fluoroquinolones, including levofloxacin, in patients who experience any of these serious adverse reactions [see Warnings and Precautions (5.1)]
• Fluoroquinolones, including levofloxacin, may exacerbate muscle weakness in patients with myasthenia gravis. Avoid levofloxacin in patients with a known history of myasthenia gravis [see Warnings and Precautions (5.5)].
• Because fluoroquinolones, including levofloxacin, have been associated with serious adverse reactions [see Warnings and Precautions (5.1 to 5.15)], reserve levofloxacin for use in patients who have no alternative treatment options for the following indications:
o Uncomplicated urinary tract infection [see Indications and Usage (1.12)]
o Acute bacterial exacerbation of chronic bronchitis [see Indications and Usage (1.13)]
o Acute bacterial sinusitis [see Indications and Usage (1.14)].

1 INDICATIONS AND USAGE

1.1 Nosocomial Pneumonia

Levofloxacin tablets are indicated in adult patients for the treatment of nosocomial pneumonia due to methicillin-susceptible Staphylococcus aureus, Pseudomonas aeruginosa, Serratia marcescens, Escherichia coli, Klebsiella pneumoniae, Haemophilus influenzae,or Streptococcus pneumoniae.Adjunctive therapy should be used as clinically indicated. Where Pseudomonas aeruginosais a documented or presumptive pathogen, combination therapy with an anti-pseudomonal β-lactam is recommended [see Clinical Studies (14.1)].

1.2 Community-Acquired Pneumonia: 7 to 14 day Treatment Regimen

Levofloxacin tablets are indicated in adult patients for the treatment of community-acquired pneumonia due to methicillin-susceptible Staphylococcus aureus, Streptococcus pneumoniae(including multi-drug-resistant Streptococcus pneumoniae[MDRSP]), Haemophilus influenzae, Haemophilus parainfluenzae, Klebsiella pneumoniae, Moraxella catarrhalis, Chlamydophila pneumoniae, Legionella pneumophila,or Mycoplasma pneumoniae [see Dosage and Administration (2.1) and Clinical Studies (14.2)].
MDRSP isolates are isolates resistant to two or more of the following antibacterials: penicillin (MIC ≥2 mcg/mL), 2ndgeneration cephalosporins, e.g., cefuroxime, macrolides, tetracyclines and trimethoprim/sulfamethoxazole.

1.3 Community-Acquired Pneumonia: 5-day Treatment Regimen

Levofloxacin tablets are indicated in adult patients for the treatment of community-acquired pneumonia due to Streptococcus pneumoniae(excluding multi-drug-resistant isolates [MDRSP]), Haemophilus influenzae, Haemophilus parainfluenzae, Mycoplasma pneumoniae,or Chlamydophila pneumoniae [see Dosage and Administration (2.1) and Clinical Studies (14.3)].

1.4 Complicated Skin and Skin Structure Infections

Levofloxacin tablets are indicated in adult patients for the treatment of complicated skin and skin structure infections due to methicillin-susceptible Staphylococcus aureus, Enterococcus faecalis, Streptococcus pyogenes,or Proteus mirabilis [see Clinical Studies (14.5)].

1.5 Uncomplicated Skin and Skin Structure Infections

Levofloxacin tablets are indicated in adult patients for the treatment of uncomplicated skin and skin structure infections (mild to moderate) including abscesses, cellulitis, furuncles, impetigo, pyoderma, wound infections, due to methicillin-susceptible Staphylococcus aureus,or Streptococcus pyogenes.

1.6 Chronic Bacterial Prostatitis

Levofloxacin tablets are indicated in adult patients for the treatment of chronic bacterial prostatitis due to Escherichia coli, Enterococcus faecalis,or methicillin-susceptible Staphylococcus epidermidis [see Clinical Studies (14.6)].

1.7 Inhalational Anthrax (Post-Exposure)

Levofloxacin tablets are indicated for inhalational anthrax (post-exposure) to reduce the incidence or progression of disease following exposure to aerosolized Bacillus anthracisin adults and pediatric patients, 6 months of age and older [see Dosage and Administration (2.2)]. The effectiveness of levofloxacin tablets is based on plasma concentrations achieved in humans, a surrogate endpoint reasonably likely to predict clinical benefit.
Levofloxacin tablets have not been tested in humans for the post-exposure prevention of inhalation anthrax. The safety of levofloxacin tablets in adults for durations of therapy beyond 28 days or in pediatric patients for durations of therapy beyond 14 days has not been studied. Prolonged levofloxacin tablets therapy should only be used when the benefit outweighs the risk [see Clinical Studies (14.9)].

1.8 Plague

Levofloxacin tablets are indicated for treatment of plague, including pneumonic and septicemic plague, due to Yersinia pestis(Y. pestis) and prophylaxis for plague in adults and pediatric patients, 6 months of age and older [see Dosage and Administration (2.2)].
Efficacy studies of levofloxacin tablets could not be conducted in humans with plague for ethical and feasibility reasons. Therefore, approval of this indication was based on an efficacy study conducted in animals [see Clinical Studies (14.10)].

1.9 Complicated Urinary Tract Infections: 5-day Treatment Regimen

Levofloxacin tablets are indicated in adult patients for the treatment of complicated urinary tract infections due to Escherichia coli, Klebsiella pneumoniae,or Proteus mirabilis [see Clinical Studies (14.7)].

1.10 Complicated Urinary Tract Infections: 10-day Treatment Regimen

Levofloxacin tablets are indicated in adult patients for the treatment of complicated urinary tract infections (mild to moderate) due to Enterococcus faecalis, Enterobacter cloacae, Escherichia coli, Klebsiella pneumoniae, Proteus mirabilis,or Pseudomonas aeruginosa [see Clinical Studies (14.8)].

1.11 Acute Pyelonephritis: 5 or 10-day Treatment Regimen

Levofloxacin tablets are indicated in adult patients for the treatment of acute pyelonephritis caused by Escherichia coli,including cases with concurrent bacteremia [see Clinical Studies (14.7, 14.8)].

1.12 Uncomplicated Urinary Tract Infections

Levofloxacin tablets are indicated in adult patients for the treatment of uncomplicated urinary tract infections (mild to moderate) due to Escherichia coli, Klebsiella pneumoniae,or Staphylococcus saprophyticus.
Because fluoroquinolones, including levofloxacin tablets, have been associated with serious adverse reactions [see Warnings and Precautions (5.1 to 5.15)] and for some patients uncomplicated urinary tract infection is self-limiting, reserve levofloxacin tablets for treatment of uncomplicated urinary tract infections in patients who have no alternative treatment options.

1.13 Acute Bacterial Exacerbation of Chronic Bronchitis

Levofloxacin tablets are indicated in adult patients for the treatment of acute bacterial exacerbation of chronic bronchitis (ABECB) due to

methicillin-susceptible Staphylococcus aureus, Streptococcus pneumoniae, Haemophilus influenzae, Haemophilus parainfluenzae,or Moraxella catarrhalis.
Because fluoroquinolones, including levofloxacin tablets, have been associated with serious adverse reactions [see Warnings and Precautions (5.1to 5.15)] and for some patients ABECB is self-limiting, reserve levofloxacin tablets for treatment of ABECB in patients who have no alternative treatment options.

1.14 Acute Bacterial Sinusitis: 5-day and 10 to 14 day Treatment Regimens

Levofloxacin tablets are indicated in adult patients for the treatment of acute bacterial sinusitis (ABS) due

to Streptococcus pneumoniae, Haemophilus influenzae,or Moraxella catarrhalis [see Clinical Studies (14.4)].
Because fluoroquinolones, including levofloxacin tablets, have been associated with serious adverse reactions [see Warnings and Precautions (5.1to 5.15)] and for some patients ABS is self-limiting, reserve levofloxacin tablets for treatment of ABS in patients who have no alternative treatment options.

1.15 Usage

To reduce the development of drug-resistant bacteria and maintain the effectiveness of levofloxacin tablets and other antibacterial drugs, levofloxacin tablets should be used only to treat or prevent infections that are proven or strongly suspected to be caused by susceptible bacteria. When culture and susceptibility information are available, they should be considered in selecting or modifying antibacterial therapy. In the absence of such data, local epidemiology and susceptibility patterns may contribute to the empiric selection of therapy.
Culture and susceptibility testing
Appropriate culture and susceptibility tests should be performed before treatment in order to isolate and identify organisms causing the infection and to determine their susceptibility to levofloxacin [see Microbiology (12.4)] .Therapy with levofloxacin tablets may be initiated before results of these tests are known; once results become available, appropriate therapy should be selected.
As with other drugs in this class, some isolates of Pseudomonas aeruginosamay develop resistance fairly rapidly during treatment with levofloxacin tablets. Culture and susceptibility testing performed periodically during therapy will provide information about the continued susceptibility of the pathogens to the antimicrobial agent and also the possible emergence of bacterial resistance.

2 DOSAGE AND ADMINISTRATION

2.1 Dosage of Levofloxacin Tablets in Adult Patients with Creatinine Clearance ≥ 50 mL/minute

The usual dose of levofloxacin tablets is 250 mg, 500 mg, or 750 mg administered orally every 24 hours, as indicated by infection and described in Table 1. These recommendations apply to patients with creatinine clearance ≥ 50 mL/minute. For patients with creatinine clearance less than 50 mL/min, adjustments to the dosing regimen are required [see Dosage and Administration (2.3)].
Table 1: Dosage of Levofloxacin Tablets in Adult Patients with Creatinine Clearance greater than or equal to 50 mL/minute)

Type of Infection* | Dosed Every 24 hours | Duration (days)†
Nosocomial Pneumonia | 750 mg | 7 to 14
Community Acquired Pneumonia‡ | 500 mg‡ | 7 to 14‡
Community Acquired Pneumonia§ | 750 mg§ | 5§
Complicated Skin and Skin Structure Infections (SSSI) | 750 mg | 7 to 14
Uncomplicated SSSI | 500 mg | 7 to 10
Chronic Bacterial Prostatitis | 500 mg | 28
Inhalational Anthrax (Post-Exposure), adult and pediatric patients weighing 50 kgÞ,ßor greater Pediatric patients weighing 30 kg to less than 50 kgÞ,ß | 500 mg see Table 2 below (2.2) | 60ß 60ß
Plague, adult and pediatric patients weighing 50 kgàor greater Pediatric patients weighing 30 kg to less than 50 kg | 500 mg see Table 2 below (2.2) | 10 to 14 10 to 14
Complicated Urinary Tract Infection (cUTI) or Acute Pyelonephritis (AP)¶ | 750 mg | 5
Complicated Urinary Tract Infection (cUTI) or Acute Pyelonephritis (AP)# | 250 mg# | 10#
Uncomplicated Urinary Tract Infection | 250 mg | 3
Acute Bacterial Exacerbation of Chronic Bronchitis (ABECB) | 500 mg | 7
Acute Bacterial Sinusitis (ABS) | 750 mg | 5
Acute Bacterial Sinusitis (ABS) | 500 mg | 10 to 14

*Due to the designated pathogens [see Indications and Usage (1)].
†Sequential therapy (intravenous levofloxacin to oral levofloxacin tablets) may be instituted at the discretion of the healthcare provider.
‡Due to methicillin-susceptible Staphylococcus aureus, Streptococcus pneumoniae(including multi-drug-resistant isolates [MDRSP]), Haemophilus influenzae, Haemophilus parainfluenzae, Klebsiella pneumoniae, Moraxella catarrhalis, Chlamydophila pneumoniae, Legionella pneumophila,or Mycoplasma pneumoniae [see Indications and Usage (1.2)].
§Due to Streptococcus pneumoniae(excluding multi-drug-resistant isolates [MDRSP]), Haemophilus influenzae, Haemophilus parainfluenzae, Mycoplasma pneumoniae, or Chlamydophila pneumoniae [see Indications and Usage (1.3)].
¶This regimen is indicated for cUTI due to Escherichia coli, Klebsiella pneumoniae, Proteus mirabilisand AP due to E. coli,including cases with concurrent bacteremia.
#This regimen is indicated for cUTI due to Enterococcus faecalis, Enterococcus cloacae, Escherichia coli, Klebsiella pneumoniae, Proteus mirabilis, Pseudomonas aeruginosa;and for AP due to E. coli.
ÞDrug administration should begin as soon as possible after suspected or confirmed exposure to aerosolized B. anthracis. This indication is based on a surrogate endpoint. Levofloxacin plasma concentrations achieved in humans are reasonably likely to predict clinical benefit [see Clinical Studies (14.9)].
ßThe safety of levofloxacin tablets in adults for durations of therapy beyond 28 days or in pediatric patients for durations beyond 14 days has not been studied. An increased incidence of musculoskeletal adverse events compared to controls has been observed in pediatric patients [see Warnings and Precautions (5.12) , Use in Specific Populations (8.4), and Clinical Studies (14.9)]. Prolonged levofloxacin tablets therapy should only be used when the benefit outweighs the risk.
àDrug administration should begin as soon as possible after suspected or confirmed exposure to Yersinia pestis. Higher doses of levofloxacin tablets typically used for treatment of pneumonia can be used for treatment of plague, if clinically indicated.

2.2 Dosage of Levofloxacin Tablets in Pediatric Patients with Inhalational Anthrax or Plague

The dosage of levofloxacin tablets for inhalational anthrax (post-exposure) and plague in pediatric patients who weigh 30 kg or greater is described below in Table 2. Levofloxacin tablets cannot be administered to patients who weigh less than 30 kg because of the limitations of the available strength. Alternative formulations of levofloxacin may be considered for pediatric patients who weigh less than 30 kg.

Table 2 Levofloxacin Tablets Dosage in Pediatric Patients Weighing 30 kg or greater with Inhalational Anthrax (Post-Exposure) and Plague*

Type of Infection* | Dose | Frequency | Duration †
Inhalational Anthrax (post-exposure)‡,§
Pediatric patients weighing 50 kg or greater | 500 mg | every 24 hours | 60 days§
Pediatric patients weighing 30 kg to less than 50 kg | 250 mg | every 12 hours | 60 days§
Plague¶
Pediatric patients weighing 50 kg or greater | 500 mg | every 24 hours | 10 to 14 days
Pediatric patients weighing 30 kg to less than 50 kg | 250 mg | every 12 hours | 10 to 14 days

*Due to Bacillus anthracis [see Indications and Usage (1.13)] and Yersinia pestis [see Indications and Usage (1.14)].

†Sequential therapy (intravenous levofloxacin injection to oral levofloxacin tablets) may be instituted at the discretion of the healthcare provider.
‡Begin levofloxacin tablets as soon as possible after suspected or confirmed exposure to aerosolized B. anthracis.
§The safety of levofloxacin tablets in pediatric patients for durations of therapy beyond 14 days has not been studied. [see Warnings and Precautions (5.12), Use in SpecificPopulations (8.4), and Clinical Studies (14.9)] . Begin levofloxacin tablets as soon as possible after suspected or confirmed exposure to Yersinia pestis.

2.3 Dosage Adjustment in Adults with Renal Impairment

Administer levofloxacin tablets with caution in patients with renal impairment. Careful clinical observation and appropriate laboratory studies should be performed prior to and during therapy since elimination of levofloxacin may be reduced in these patients.
In patients with renal impairment (creatinine clearance less than 50 mL/min), adjustment of the dosage regimen is necessary to avoid the accumulation of levofloxacin due to decreased clearance [see Use in Specific Populations (8.6)]. No adjustment is necessary for patients with a creatinine clearance greater than or equal to 50 mL/minute.
Table 3 shows how to adjust dose based on creatinine clearance.
Table 3: Dosage Adjustment in Adult Patients with Renal Impairment (Creatinine Clearance less than 50 mL/minute)

Creatinine Clearance greater than or equal to 50 mL/minute | Creatinine Clearance 20 to 49 mL/minute | Creatinine Clearance 10 to 19 mL/minute | Hemodialysis or Chronic Ambulatory Peritoneal Dialysis (CAPD)
750 mg every 24 hours | 750 mg every 48 hours | 750 mg initial dose, then 500 mg every 48 hours | 750 mg initial dose, then 500 mg every 48 hours
500 mg every 24 hours | 500 mg initial dose, then 250 mg every 24 hours | 500 mg initial dose, then 250 mg every 48 hours | 500 mg initial dose, then 250 mg every 48 hours
250 mg every 24 hours | No dosage adjustment required | 250 mg every 48 hours. If treating uncomplicated UTI, then no dosage adjustment is required | No information on dosing adjustment is available

2.4 Drug Interaction With Chelation Agents: Antacids, Sucralfate, Metal Cations, Multivitamins

Levofloxacin tablets should be administered at least two hours before or two hours after antacids containing magnesium, aluminum, as well as sucralfate, metal cations such as iron, and multivitamin preparations with zinc or didanosine chewable/buffered tablets or the pediatric powder for oral solution [see Drug Interactions (7.1)and Patient Counseling Information (17)].

2.5 Important Administration Instructions

Levofloxacin tablets can be administered without regard to food.
If patients miss a dose, they should take it as soon as possible anytime up to 8 hours prior to their next scheduled dose. If less than 8 hours remain before the next dose, wait until their next scheduled dose.

2.6 Hydration for Patients Receiving Levofloxacin Tablets

Adequate hydration of patients receiving levofloxacin should be maintained to prevent the formation of highly concentrated urine. Crystalluria and cylindruria have been reported with quinolones [see Adverse Reactions (6.1) and Patient Counseling Information (17)].

3 DOSAGE FORMS AND STRENGTHS

• Levofloxacin tablets, USP 750 mg are white colored, capsule shaped, biconvex, film coated tablets debossed with '18' on one side and 'I' on the other side.

4 CONTRAINDICATIONS

Levofloxacin tablets are contraindicated in persons with known hypersensitivity to levofloxacin, or other quinolone antibacterials [see Warnings and Precautions (5.3)].

5 WARNINGS AND PRECAUTIONS

5.1 Disabling and Potentially Irreversible Serious Adverse Reactions Including Tendinitis and Tendon Rupture, Peripheral Neuropathy, and Central Nervous System Effects

Fluoroquinolones, including levofloxacin, have been associated with disabling and potentially irreversible serious adverse reactions from different body systems that can occur together in the same patient. Commonly seen adverse reactions include tendinitis, tendon rupture, arthralgia, myalgia, peripheral neuropathy, and central nervous system effects (hallucinations, anxiety, depression, insomnia, severe headaches, and confusion). These reactions can occur within hours to weeks after starting levofloxacin. Patients of any age or without pre-existing risk factors have experienced these adverse reactions [see Warnings and Precautions (5.2, 5.3, 5.4)].
Discontinue levofloxacin immediately at the first signs or symptoms of any serious adverse reaction. In addition, avoid the use of fluoroquinolones, including levofloxacin, in patients who have experienced any of these serious adverse reactions associated with fluoroquinolones.

5.2 Tendinitis and Tendon Rupture

Fluoroquinolones, including levofloxacin, have been associated with an increased risk of tendinitis and tendon rupture in all ages [see Warnings and Precautions (5.1) and Adverse Reactions (6.2)] . This adverse reaction most frequently involves the Achilles tendon and has also been reported with the rotator cuff (the shoulder), the hand, the biceps, the thumb, and other tendon sites. Tendinitis or tendon rupture can occur within hours or days of starting levofloxacin or as long as several months after completion of fluoroquinolone therapy. Tendinitis and tendon rupture can occur bilaterally.
The risk of developing fluoroquinolone-associated tendinitis and tendon rupture is increased in patients over 60 years of age, in those taking corticosteroid drugs, and in patients with kidney, heart or lung transplants. Other factors that may independently increase the risk of tendon rupture include strenuous physical activity, renal failure, and previous tendon disorders such as rheumatoid arthritis. Tendinitis and tendon rupture have been reported in patients taking fluoroquinolones who do not have the above risk factors. Discontinue levofloxacin immediately if the patient experiences pain, swelling, inflammation or rupture of a tendon. Patients should be advised to rest at the first sign of tendinitis or tendon rupture, and to contact their healthcare provider regarding changing to a non-quinolone antimicrobial drug. Avoid levofloxacin in patients who have a history of tendon disorders or tendon rupture [see Adverse Reactions (6.2) and Patient Counseling Information (17)].

5.3 Peripheral Neuropathy

Fluoroquinolones, including levofloxacin, have been associated with an increased risk of peripheral neuropathy. Cases of sensory or sensorimotor axonal polyneuropathy affecting small and/or large axons resulting in paresthesias, hypoesthesias, dysesthesias and weakness have been reported in patients receiving fluoroquinolones, including levofloxacin. Symptoms may occur soon after initiation of levofloxacin and may be irreversible in some patients [see Warnings and Precautions (5.1) and Adverse Reactions (6.1,6.2)].
Discontinue levofloxacin immediately if the patient experiences symptoms of neuropathy including pain, burning, tingling, numbness, and/or weakness or other alterations of sensation including light touch, pain, temperature, position sense, and vibratory sensation. Avoid fluoroquinolones, including levofloxacin, in patients who have previously experienced peripheral neuropathy [see Adverse Reactions (6)and Patient Counseling Information (17)] .

5.4 Central Nervous System Effects

Psychiatric Adverse Reactions
Fluoroquinolones, including levofloxacin, have been associated with an increased risk of psychiatric adverse reactions, including: toxic psychoses, hallucinations, or paranoia; depression, or suicidal thoughts; anxiety, agitation, restlessness, or nervousness; confusion, delirium, disorientation, or disturbances in attention; insomnia or nightmares; memory impairment. Attempted or completed suicide have been reported, especially in patients with a medical history of depression, or an underlying risk factor for depression. These reactions may occur following the first dose. If these reactions occur in patients receiving levofloxacin, discontinue levofloxacin and institute appropriate measures.
Central Nervous System Adverse Reactions
Fluoroquinolones, including levofloxacin, have been associated with an increased risk of seizures (convulsions), increased intracranial pressure (including pseudotumor cerebri), tremors, and lightheadedness. As with other fluoroquinolones, levofloxacin should be used with caution in patients with a known or suspected central nervous system (CNS) disorder that may predispose them to seizures or lower the seizure threshold (e.g., severe cerebral arteriosclerosis, epilepsy) or in the presence of other risk factors that may predispose them to seizures or lower the seizure threshold (e.g., certain drug therapy, renal dysfunction). If these reactions occur in patients receiving levofloxacin discontinue levofloxacin and institute appropriate measures [see Adverse Reactions (6), Drug Interactions (7.4,7.5), and Patient Counseling Information (17)].

5.5 Exacerbation of Myasthenia Gravis

Fluoroquinolones, including levofloxacin, have neuromuscular blocking activity and may exacerbate muscle weakness in patients with myasthenia gravis. Postmarketing serious adverse reactions including deaths and requirement for ventilatory support, have been associated with fluoroquinolone use in patients with myasthenia gravis. Avoid levofloxacin in patients with a known history of myasthenia gravis [see Adverse Reactions (6.3)and Patient Counseling Information (17)].

5.6 Other Serious and Sometimes Fatal Adverse Reactions

Other serious and sometimes fatal adverse reactions, some due to hypersensitivity, and some due to uncertain etiology, have been reported rarely in patients receiving therapy with fluoroquinolones, including levofloxacin. These events may be severe and generally occur following the administration of multiple doses. Clinical manifestations may include one or more of the following:
• fever, rash, or severe dermatologic reactions (e.g., toxic epidermal necrolysis, Stevens-Johnson Syndrome);
• vasculitis; arthralgia; myalgia; serum sickness;
• allergic pneumonitis;
• interstitial nephritis; acute renal insufficiency or failure;
• hepatitis; jaundice; acute hepatic necrosis or failure;
• anemia, including hemolytic and aplastic; thrombocytopenia, including thrombotic thrombocytopenic purpura; leukopenia; agranulocytosis; pancytopenia; and/or other hematologic abnormalities.
Discontinue levofloxacin immediately at the first appearance of skin rash, jaundice, or any other sign of hypersensitivity and institute supportive measures [see Adverse Reactions (6) and Patient Counseling Information (17)].

5.7 Hypersensitivity Reactions

Serious and occasionally fatal hypersensitivity and/or anaphylactic reactions have been reported in patients receiving therapy with fluoroquinolones, including levofloxacin. These reactions often occur following the first dose. Some reactions have been accompanied by cardiovascular collapse, acute myocardial ischemia with or without myocardial infraction, hypotension/shock, seizure, loss of consciousness, tingling, angioedema (including tongue, laryngeal, throat, or facial edema/swelling), airway obstruction (including bronchospasm, shortness of breath, and acute respiratory distress), dyspnea, urticaria, itching, and other serious skin reactions. Levofloxacin should be discontinued immediately at the first appearance of a skin rash or any other sign of hypersensitivity. Serious acute hypersensitivity reactions may require treatment with epinephrine and other resuscitative measures, including oxygen, intravenous fluids, antihistamines, corticosteroids, pressor amines, and airway management, as clinically indicated [see Adverse Reactions (6)and Patient Counseling Information (17)].

5.8 Hepatotoxicity

Epidemiologic studies report an increased rate of aortic aneurysm and dissection within two months following use of fluoroquinolones, particularly in elderly patients. The cause for the increased risk has not been identified. In patients with a known aortic aneurysm or patients who are at greater risk for aortic aneurysms, reserve levofloxacin for use only when there are no alternative antibacterial treatments available.

5.9 Risk of Aortic Aneurysm and Dissection

Post-marketing reports of severe hepatotoxicity (including acute hepatitis and fatal events) have been received for patients treated with levofloxacin. No evidence of serious drug-associated hepatotoxicity was detected in clinical trials of over 7,000 patients. Severe hepatotoxicity generally occurred within 14 days of initiation of therapy and most cases occurred within 6 days. Most cases of severe hepatotoxicity were not associated with hypersensitivity [see Warnings and Precautions (5.6)]. The majority of fatal hepatotoxicity reports occurred in patients 65 years of age or older and most were not associated with hypersensitivity. Levofloxacin should be discontinued immediately if the patient develops signs and symptoms of hepatitis [see Adverse Reactions (6) and Patient Counseling Information (17)].

5.10 Clostridium difficile-Associated Diarrhea

Clostridium difficile-associated diarrhea (CDAD) has been reported with use of nearly all antibacterial agents, including levofloxacin, and may range in severity from mild diarrhea to fatal colitis. Treatment with antibacterial agents alters the normal flora of the colon leading to overgrowth of C. difficile.
C. difficileproduces toxins A and B which contribute to the development of CDAD. Hypertoxin producing strains of C. difficilecause increased morbidity and mortality, as these infections can be refractory to antimicrobial therapy and may require colectomy. CDAD must be considered in all patients who present with diarrhea following antibiotic use. Careful medical history is necessary since CDAD has been reported to occur over two months after the administration of antibacterial agents.
If CDAD is suspected or confirmed, ongoing antibiotic use not directed against C. difficilemay need to be discontinued. Appropriate fluid and electrolyte management, protein supplementation, antibiotic treatment of C. difficile, and surgical evaluation should be instituted as clinically indicated [see Adverse Reactions (6.2) and Patient Counseling Information (17)].

5.11 Prolongation of the QT Interval

Some fluoroquinolones, including levofloxacin, have been associated with prolongation of the QT interval on the electrocardiogram and infrequent cases of arrhythmia. Rare cases of torsade de pointes have been spontaneously reported during postmarketing surveillance in patients receiving fluoroquinolones, including levofloxacin. Levofloxacin should be avoided in patients with known prolongation of the QT interval, patients with uncorrected hypokalemia, and patients receiving Class IA (quinidine, procainamide), or Class III (amiodarone, sotalol) antiarrhythmic agents. Elderly patients may be more susceptible to drug-associated effects on the QT interval [see Adverse Reactions (6.3) , Use in Specific Populations (8.5),and Patient Counseling Information (17)].

5.12 Musculoskeletal Disorders in Pediatric Patients and Arthropathic Effects in Animals

Levofloxacin is indicated in pediatric patients (6 months of age and older) only for the prevention of inhalational anthrax (post-exposure) and for plague [see Indications and Usage (1.7, 1.8)]. An increased incidence of musculoskeletal disorders (arthralgia, arthritis, tendinopathy, and gait abnormality) compared to controls has been observed in pediatric patients receiving levofloxacin [see Use in Specific Populations (8.4)].
In immature rats and dogs, the oral and intravenous administration of levofloxacin resulted in increased osteochondrosis. Histopathological examination of the weight-bearing joints of immature dogs dosed with levofloxacin revealed persistent lesions of the cartilage. Other fluoroquinolones also produce similar erosions in the weight-bearing joints and other signs of arthropathy in immature animals of various species [see Animal Toxicology and/or Pharmacology (13.2)].

5.13 Blood Glucose Disturbances

Fluoroquinolones, including levofloxacin, have been associated with disturbances of blood glucose, including symptomatic hyperglycemia and hypoglycemia, usually in diabetic patients receiving concomitant treatment with an oral hypoglycemic agent (e.g., glyburide) or with insulin. In these patients, careful monitoring of blood glucose is recommended. Severe cases of hypoglycemia resulting in coma or death have been reported. If a hypoglycemic reaction occurs in a patient being treated with levofloxacin, discontinue levofloxacin and initiate appropriate therapy immediately [see Adverse Reactions (6.2), Drug Interactions (7.3) and Patient Counseling Information (17)].

5.14 Photosensitivity/Phototoxicity

Moderate to severe photosensitivity/phototoxicity reactions, the latter of which may manifest as exaggerated sunburn reactions (e.g., burning, erythema, exudation, vesicles, blistering, edema) involving areas exposed to light (typically the face, “V” area of the neck, extensor surfaces of the forearms, dorsa of the hands), can be associated with the use of fluoroquinolones after sun or UV light exposure. Therefore, excessive exposure to these sources of light should be avoided. Drug therapy should be discontinued if photosensitivity/phototoxicity occurs [see Adverse Reactions (6.3) and Patient Counseling Information (17)].

5.15 Development of Drug Resistant Bacteria

Prescribing levofloxacin in the absence of a proven or strongly suspected bacterial infection or a prophylactic indication is unlikely to provide benefit to the patient and increases the risk of the development of drug-resistant bacteria [see Patient Counseling Information (17)].

6 ADVERSE REACTIONS

The following serious and otherwise important adverse drug reactions are discussed in greater detail in other sections of labeling:
• Disabling and Potentially Irreversible Serious Adverse Reactions [see Warnings and Precautions (5.1)]
• Tendinitis and Tendon Rupture [see Warnings and Precautions (5.2)]
• Peripheral Neuropathy [see Warnings and Precautions (5.3)]
• Central Nervous System Effects [see Warnings and Precautions (5.4)]
• Exacerbation of Myasthenia Gravis [see Warnings and Precautions (5.5)]
• Other Serious and Sometimes Fatal Reactions [see Warnings and Precautions (5.6)]
• Hypersensitivity Reactions [see Warnings and Precautions (5.7)]
• Hepatotoxicity [see Warnings and Precautions (5.8)]
• Risk of Aortic Aneurysm and Dissection [see Warnings and Precautions (5.9)]
• Clostridium difficile-Associated Diarrhea [see Warnings and Precautions (5.10)]
• Prolongation of the QT Interval [see Warnings and Precautions (5.11)]
• Musculoskeletal Disorders in Pediatric Patients [see Warnings and Precautions (5.12)]
• Blood Glucose Disturbances [see Warnings and Precautions (5.13)]
• Photosensitivity/Phototoxicity [see Warnings and Precautions (5.14)]
• Development of Drug Resistant Bacteria [see Warnings and Precautions (5.15)]
Crystalluria and cylindruria have been reported with quinolones, including levofloxacin. Therefore, adequate hydration of patients receiving levofloxacin should be maintained to prevent the formation of a highly concentrated urine [see Dosage and Administration (2.5)].

6.1 Clinical Trial Experience

Because clinical trials are conducted under widely varying conditions, adverse reaction rates observed in the clinical trials of a drug cannot be directly compared to rates in the clinical trials of another drug and may not reflect the rates observed in practice.
The data described below reflect exposure to levofloxacin in 7537 patients in 29 pooled Phase 3 clinical trials. The population studied had a mean age of 50 years (approximately 74% of the population was < 65 years of age), 50% were male, 71% were Caucasian, 19% were Black. Patients were treated with levofloxacin for a wide variety of infectious diseases [see Indications and Usage (1)]. Patients received levofloxacin doses of 750 mg once daily, 250 mg once daily, or 500 mg once or twice daily. Treatment duration was usually 3 to 14 days, and the mean number of days on therapy was 10 days.
The overall incidence, type and distribution of adverse reactions was similar in patients receiving levofloxacin doses of 750 mg once daily, 250 mg once daily, and 500 mg once or twice daily. Discontinuation of levofloxacin due to adverse drug reactions occurred in 4.3% of patients overall, 3.8% of patients treated with the 250 mg and 500 mg doses and 5.4% of patients treated with the 750 mg dose. The most common adverse drug reactions leading to discontinuation with the 250 and 500 mg doses were gastrointestinal (1.4%), primarily nausea (0.6%); vomiting (0.4%); dizziness (0.3%); and headache (0.2%). The most common adverse drug reactions leading to discontinuation with the 750 mg dose were gastrointestinal (1.2%), primarily nausea (0.6%), vomiting (0.5%); dizziness (0.3%); and headache (0.3%).
Adverse reactions occurring in ≥1% of levofloxacin-treated patients and less common adverse reactions, occurring in 0.1 to <1% of levofloxacin-treated patients, are shown in Table 4 and Table 5, respectively. The most common adverse drug reactions (≥3%) are nausea, headache, diarrhea, insomnia, constipation, and dizziness.
Table 4: Common (≥1%) Adverse Reactions Reported in Clinical Trials with Levofloxacin#

System/Organ Class | Adverse Reaction | % (N=7,537)
Infections and Infestations | moniliasis | 1
Psychiatric Disorders | insomnia*[see Warnings and Precautions (5.4)] | 4
Nervous System Disorders | headache dizziness [see Warnings and Precautions (5.4)] | 6 3
Respiratory, Thoracic and Mediastinal Disorders | dyspnea [see Warnings and Precautions (5.7)] | 1
Gastrointestinal Disorders | nausea diarrhea constipation abdominal pain vomiting dyspepsia | 7 5 3 2 2 2
Skin and Subcutaneous Tissue Disorders | rash [see Warnings and Precautions (5.7)] pruritus | 2 1
Reproductive System and Breast Disorders | Vaginitis | 1†
General Disorders and Administration Site Conditions | edema injection site reaction chest pain | 1 1 1

*N = 7,274
†N = 3,758 (women)
#pool of studies included IV and oral administration
Table 5: Less Common (0.1 to 1%) Adverse Reactions Reported in Clinical Trials with Levofloxacin (N=7,537)

System/Organ Class | Adverse Reaction
Infections and Infestations | genital moniliasis
Blood and Lymphatic System Disorders | anemia thrombocytopenia granulocytopenia [see Warnings and Precautions (5.6)]
Immune System Disorders | allergic reaction [see Warnings and Precautions (5.6, 5.7)]
Metabolism and Nutrition Disorders | hyperglycemia hypoglycemia [see Warnings and Precautions (5.13)] hyperkalemia
Psychiatric Disorders | anxiety agitation confusion depression hallucination nightmare* [see Warnings and Precautions (5.4)] sleep disorder* anorexia abnormal dreaming*
Nervous System Disorders | tremor convulsions [see Warnings and Precautions (5.4)] paresthesia [see Warnings and Precautions (5.3)] vertigo hypertonia hyperkinesias abnormal gait somnolence* syncope
Respiratory, Thoracic and Mediastinal Disorders | epistaxis
Cardiac Disorders | cardiac arrest palpitation ventricular tachycardia ventricular arrhythmia
Vascular Disorders | phlebitis
Gastrointestinal Disorders | gastritis stomatitis pancreatitis esophagitis gastroenteritis glossitis pseudomembranous/ C. difficilecolitis [see Warnings and Precautions (5.10)]
Hepatobiliary Disorders | abnormal hepatic function increased hepatic enzymes increased alkaline phosphatase
Skin and Subcutaneous Tissue Disorders | urticaria [see Warnings and Precautions (5.7)]
Musculoskeletal and Connective Tissue Disorders | arthralgia tendinitis [see Warnings and Precautions (5.2)] myalgia skeletal pain
Renal and Urinary Disorders | abnormal renal function acute renal failure [see Warnings and Precautions (5.6)]

*N = 7,274
In clinical trials using multiple-dose therapy, ophthalmologic abnormalities, including cataracts and multiple punctate lenticular opacities, have been noted in patients undergoing treatment with quinolones, including levofloxacin. The relationship of the drugs to these events is not presently established.

6.2 Postmarketing Experience

Table 6 lists adverse reactions that have been identified during post-approval use of levofloxacin. Because these reactions are reported voluntarily from a population of uncertain size, it is not always possible to reliably estimate their frequency or establish a causal relationship to drug exposure.
Table 6: Postmarketing Reports Of Adverse Drug Reactions

System/Organ Class | Adverse Reaction
Blood and Lymphatic System Disorders | pancytopenia aplastic anemia leukopenia hemolytic anemia [see Warnings and Precautions (5.6)] eosinophilia
Immune System Disorders | hypersensitivity reactions, sometimes fatal including: anaphylactic/anaphylactoid reactions anaphylactic shock angioneurotic edema serum sickness [see Warnings and Precautions (5.6, 5.7)]
Psychiatric Disorders | psychosis paranoia isolated reports of suicidal ideation, suicide attempt and completed suicide [see Warnings and Precautions (5.4)]
Nervous System Disorders | exacerbation of myasthenia gravis [see Warnings and Precautions (5.5)] anosmia ageusia parosmia dysgeusia peripheral neuropathy (may be irreversible) [see Warnings and Precautions (5.3)] isolated reports of encephalopathy abnormal electroencephalogram (EEG) dysphonia pseudotumor cerebri [see Warnings and Precautions (5.4)]
Eye Disorders | uveitis vision disturbance, including diplopia visual acuity reduced vision blurred scotoma
Ear and Labyrinth Disorders | hypoacusis tinnitus
Cardiac Disorders | isolated reports of torsade de pointes electrocardiogram QT prolonged [see Warnings and Precautions (5.11)] tachycardia Acute myocardial ischemia with or without myocardial infarction occurring as part of an allergic reaction
Vascular Disorders | vasodilatation
Respiratory, Thoracic and Mediastinal Disorders | isolated reports of allergic pneumonitis [see Warnings and Precautions (5.6)]
Hepatobiliary Disorders | hepatic failure (including fatal cases) hepatitis jaundice [see Warnings and Precautions (5.6), (5.8)]
Skin and Subcutaneous Tissue Disorders | bullous eruptions to include: Stevens-Johnson Syndrome toxic epidermal necrolysis Acute Generalized Exanthematous Pustulosis (AGEP) fixed drug eruptions erythema multiforme [see Warnings and Precautions (5.6)] photosensitivity/phototoxicity reaction [see Warnings and Precautions (5.14)] leukocytoclastic vasculitis
Musculoskeletal and Connective Tissue Disorders | tendon rupture [see Warnings and Precautions (5.2)] muscle injury, including rupture rhabdomyolysis
Renal and Urinary Disorders | interstitial nephritis [see Warnings and Precautions (5.6)]
General Disorders and Administration Site Conditions | multi-organ failure pyrexia
Investigations | prothrombin time prolonged international normalized ratio prolonged muscle enzymes increased

7 DRUG INTERACTIONS

7.1 Chelation Agents: Antacids, Sucralfate, Metal Cations, Multivitamins

While the chelation by divalent cations is less marked than with other fluoroquinolones, concurrent administration of levofloxacin tablets with antacids containing magnesium, or aluminum, as well as sucralfate, metal cations such as iron, and multivitamin preparations with zinc may interfere with the gastrointestinal absorption of levofloxacin, resulting in systemic levels considerably lower than desired. Tablets with antacids containing magnesium, aluminum, as well as sucralfate, metal cations such as iron, and multivitamin preparations with zinc or didanosine may substantially interfere with the gastrointestinal absorption of levofloxacin, resulting in systemic levels considerably lower than desired. These agents should be taken at least two hours before or two hours after oral levofloxacin administration.

7.2 Warfarin

No significant effect of levofloxacin on the peak plasma concentrations, AUC, and other disposition parameters for R- and S- warfarin was detected in a clinical study involving healthy volunteers. Similarly, no apparent effect of warfarin on levofloxacin absorption and disposition was observed. However, there have been reports during the postmarketing experience in patients that levofloxacin enhances the effects of warfarin. Elevations of the prothrombin time in the setting of concurrent warfarin and levofloxacin use have been associated with episodes of bleeding. Prothrombin time, International Normalized Ratio (INR), or other suitable anticoagulation tests should be closely monitored if levofloxacin is administered concomitantly with warfarin. Patients should also be monitored for evidence of bleeding [see Adverse Reactions (6.3)and Patient Counseling Information (17)].

7.3 Antidiabetic Agents

Disturbances of blood glucose, including hyperglycemia and hypoglycemia, have been reported in patients treated concomitantly with fluoroquinolones and an antidiabetic agent. Therefore, careful monitoring of blood glucose is recommended when these agents are co-administered [see Warnings and Precautions (5.13), Adverse Reactions (6.2), and Patient Counseling Information (17)].

7.4 Non-Steroidal Anti-Inflammatory Drugs

The concomitant administration of a non-steroidal anti-inflammatory drug with a fluoroquinolone, including levofloxacin, may increase the risk of CNS stimulation and convulsive seizures [see Warnings and Precautions (5.4)].

7.5 Theophylline

No significant effect of levofloxacin on the plasma concentrations, AUC, and other disposition parameters for theophylline was detected in a clinical study involving healthy volunteers. Similarly, no apparent effect of theophylline on levofloxacin absorption and disposition was observed. However, concomitant administration of other fluoroquinolones with theophylline has resulted in prolonged elimination half-life, elevated serum theophylline levels, and a subsequent increase in the risk of theophylline-related adverse reactions in the patient population. Therefore, theophylline levels should be closely monitored and appropriate dosage adjustments made when levofloxacin is co-administered. Adverse reactions, including seizures, may occur with or without an elevation in serum theophylline levels [see Warnings and Precautions (5.4)].

7.6 Cyclosporine

No significant effect of levofloxacin on the peak plasma concentrations, AUC, and other disposition parameters for cyclosporine was detected in a clinical study involving healthy volunteers. However, elevated serum levels of cyclosporine have been reported in the patient population when co-administered with some other fluoroquinolones. Levofloxacin Cmaxand kewere slightly lower while Tmaxand t1/2were slightly longer in the presence of cyclosporine than those observed in other studies without concomitant medication. The differences, however, are not considered to be clinically significant. Therefore, no dosage adjustment is required for levofloxacin or cyclosporine when administered concomitantly.

7.7 Digoxin

No significant effect of levofloxacin on the peak plasma concentrations, AUC, and other disposition parameters for digoxin was detected in a clinical study involving healthy volunteers. Levofloxacin absorption and disposition kinetics were similar in the presence or absence of digoxin. Therefore, no dosage adjustment for levofloxacin or digoxin is required when administered concomitantly.

7.8 Probenecid and Cimetidine

No significant effect of probenecid or cimetidine on the Cmaxof levofloxacin was observed in a clinical study involving healthy volunteers. The AUC and t1/2of levofloxacin were higher while CL/F and CLRwere lower during concomitant treatment of levofloxacin with probenecid or cimetidine compared to levofloxacin alone. However, these changes do not warrant dosage adjustment for levofloxacin when probenecid or cimetidine is co-administered.

7.9 Interactions with Laboratory or Diagnostic Testing

Some fluoroquinolones, including levofloxacin, may produce false-positive urine screening results for opiates using commercially available immunoassay kits. Confirmation of positive opiate screens by more specific methods may be necessary.

8 USE IN SPECIFIC POPULATIONS

8.1 Pregnancy

Risk Summary
Published information from case reports, case control studies and observational studies on levofloxacin administered during pregnancy have not identified any drug-associated risk of major birth defects, miscarriage or adverse maternal or fetal outcomes.
In animal reproduction studies, oral administration of levofloxacin to pregnant rats and rabbits during organogenesis at doses up to 9.4 times and 1.1 times the maximum recommended human dose (MRHD), respectively, did not result in teratogenicity. Fetal toxicity was seen in the rat study, but was absent at doses up to 1.2 times the maximum recommended human dose (see Data).
The estimated background risk of major birth defects and miscarriage for the indicated population is unknown. All pregnancies have a background risk of birth defect, loss, or other adverse outcomes. In the U.S. general population, the estimated background risks of major birth defects and miscarriage in clinically recognized pregnancies is 2 to 4% and 15 to 20%, respectively.
Data
Animal Data
Levofloxacin was not teratogenic in an embryofetal development study in rats treated during organogenesis with oral doses as high as 810 mg/kg/day which corresponds to 9.4 times the MRHD (based upon doses normalized for total body surface area). The oral dose of 810 mg/kg/day (high dose) to rats caused decreased fetal body weight and increased fetal mortality that was not seen at the next lower dose (mid-dose, 90 mg/kg/day, equivalent to 1.2 times the MRHD (based upon doses normalized for total body surface area). Maternal toxicity was limited to lower weight gain in the mid and high dose groups. No teratogenicity was observed in an embryofetal development study in rabbits dosed orally during organogenesis with doses as high as 50 mg/kg/day, which corresponds to 1.1 times the MRHD (based upon doses normalized for total body surface area). Maternal toxicity at that dose consisted of lower weight gain and decreased food consumption relative to controls and abortion in four of sixteen dams.

8.2 Lactation

Risk Summary
Published literature reports that levofloxacin is present in human milk following intravenous and oral administration (see Data). There is no information regarding effects of levofloxacin on milk production or the breastfed infant. Because of the potential risks of serious adverse reactions, in breastfed infants, for most indications, a lactating woman may consider pumping and discarding breast milk during treatment with levofloxacin and an additional two days (five half-lives) after the last dose. Alternatively, advise a lactating woman that breastfeeding is not recommended during treatment with levofloxacin and for an additional two days (five half-lives) after the last dose [see Use in Specific Populations (8.4) and Clinical Pharmacology (12.3)] .
However, for inhalation anthrax (post exposure), during an incident resulting in exposure to anthrax, the risk-benefit assessment of continuing breastfeeding while the mother (and potentially the infant) is (are) on levofloxacin may be acceptable [see Dosage and Administration (2.2), Pediatric Use (8.4), and Clinical Studies (14.2)]. The developmental and health benefits of breastfeeding should be considered along with the mother’s clinical need for levofloxacin and any potential adverse effects on the breastfed child from levofloxacin or from the underlying maternal condition.
Data
A published literature reports that peak levofloxacin human milk concentration was 8.2 mg/L at 5 hours after dosing in a woman who received 500 mg of intravenous, followed by oral, levofloxacin daily. For an infant fed exclusively with human milk (approximately 900 ml/day), an estimated maximum daily dose of levofloxacin through breastfeeding is 5 mg (i.e., approximately 1% of maternal daily dose). The above data come from a single case and may not be generalizable to the general population of lactating women.

8.4 Pediatric Use

Quinolones, including levofloxacin, cause arthropathy and osteochondrosis in juvenile animals of several species. [see Warnings and Precautions (5.12) and Animal Toxicology and/or Pharmacology (13.2)].
Inhalational Anthrax (Post-Exposure)
Levofloxacin is indicated in pediatric patients 6 months of age and older, for inhalational anthrax (post-exposure). The risk-benefit assessment indicates that administration of levofloxacin to pediatric patients is appropriate. The safety of levofloxacin in pediatric patients treated for more than 14 days has not been studied [see Indications and Usage (1.7), Dosage and Administration (2.2) and Clinical Studies (14.9)].
Plague
Levofloxacin is indicated in pediatric patients, 6 months of age and older, for treatment of plague, including pneumonic and septicemic plague due to Yersinia pestis (Y. pestis)and prophylaxis for plague. Efficacy studies of levofloxacin could not be conducted in humans with pneumonic plague for ethical and feasibility reasons. Therefore, approval of this indication was based on an efficacy study conducted in animals. The risk-benefit assessment indicates that administration of levofloxacin to pediatric patients is appropriate [see Indications and Usage (1.8), Dosage and Administration (2.2) and Clinical Studies (14.10)].
Safety and effectiveness of levofloxacin in pediatric patients below the age of six months have not been established.
Pharmacokinetics following intravenous administration
The pharmacokinetics of levofloxacin following a single intravenous dose were investigated in pediatric patients ranging in age from six months to 16 years. Pediatric patients cleared levofloxacin faster than adult patients resulting in lower plasma exposures than adults for a given mg/kg dose [see Clinical Pharmacology (12.3)and Clinical Studies (14.9)].
Dosage in Pediatric Patients with Inhalational Anthrax or Plague
For the recommended levofloxacin tablet dosage in pediatric patients with inhalational anthrax or plague, see Dosage and Administration (2.2). Levofloxacin tablets cannot be administered to pediatric patients who weigh less than 30 kg because of the limitations of the available strengths. Alternative formulations of levofloxacin may be considered for pediatric patients who weigh less than 30 kg.
Adverse Reactions
In clinical trials, 1,534 pediatric patients (6 months to 16 years of age) were treated with oral and intravenous levofloxacin. Pediatric patients 6 months to 5 years of age received levofloxacin 10 mg/kg twice a day and pediatric patients greater than 5 years of age received 10 mg/kg once a day (maximum 500 mg per day) for approximately 10 days. Levofloxacin tablets can only be administered to pediatric patients with inhalational anthrax (post-exposure) or plague who are 30 kg or greater due to the limitations of the available strengths [see Dosage and Administration (2.2)].
A subset of pediatric patients in the clinical trials (1,340 levofloxacin-treated and 893 non-fluoroquinolone-treated) enrolled in a prospective, long-term surveillance study to assess the incidence of protocol-defined musculoskeletal disorders (arthralgia, arthritis, tendinopathy, gait abnormality) during 60 days and 1 year following the first dose of the study drug. Pediatric patients treated with levofloxacin had a significantly higher incidence of musculoskeletal disorders when compared to the non-fluoroquinolone-treated children as illustrated in Table 7. Levofloxacin tablets can only be administered to pediatric patients with inhalational anthrax (post-exposure) or plague who are 30 kg or greater due to the limitations of the available strengths [see Dosage and Administration (2.2)].
Table 7: Incidence of Musculoskeletal Disorders in Pediatric Clinical Trial

Follow-up Period | Levofloxacin N = 1,340 | Non-Fluoroquinolone * N = 893 | p-value †
60 days | 28 (2.1%) | 8 (0.9%) | p = 0.038
1 year ‡ | 46 (3.4%) | 16 (1.8%) | p = 0.025

*Non-Fluoroquinolone: ceftriaxone, amoxicillin/clavulanate, clarithromycin
†2-sided Fisher's Exact Test
‡ There were 1,199 levofloxacin-treated and 804 non-fluoroquinolone-treated pediatric patients who had a one-year evaluation visit. However, the incidence of musculoskeletal disorders was calculated using all reported events during the specified period for all pediatric patients enrolled regardless of whether they completed the 1-year evaluation visit.
Arthralgia was the most frequently occurring musculoskeletal disorder in both treatment groups. Most of the musculoskeletal disorders in both groups involved multiple weight-bearing joints. Disorders were moderate in 8/46 (17%) children and mild in 35/46 (76%) levofloxacin-treated pediatric patients and most were treated with analgesics. The median time to resolution was 7 days for levofloxacin-treated pediatric patients and 9 for non-fluoroquinolone-treated children (approximately 80% resolved within 2 months in both groups). No pediatric patient had a severe or serious disorder and all musculoskeletal disorders resolved without sequelae.
Vomiting and diarrhea were the most frequently reported adverse reactions, occurring in similar frequency in the levofloxacin-treated and non-fluoroquinolone-treated pediatric patients.
In addition to the

adverse reactions reported in pediatric patients in clinical trials, adverse reactions reported in adults during clinical trials or post-marketing experience [see Adverse Reactions (6)] may also be expected to occur in pediatric patients.

8.5 Geriatric Use

Geriatric patients are at increased risk for developing severe tendon disorders including tendon rupture when being treated with a fluoroquinolone such as levofloxacin. This risk is further increased in patients receiving concomitant corticosteroid therapy. Tendinitis or tendon rupture can involve the Achilles, hand, shoulder, or other tendon sites and can occur during or after completion of therapy; cases occurring up to several months after fluoroquinolone treatment have been reported. Caution should be used when prescribing levofloxacin to elderly patients especially those on corticosteroids. Patients should be informed of this potential side effect and advised to discontinue levofloxacin and contact their healthcare provider if any symptoms of tendinitis or tendon rupture occur [see Boxed Warning; Warnings and Precautions (5.2); and Adverse Reactions (6.3)].
In Phase 3 clinical trials, 1,945 levofloxacin-treated patients (26%) were ≥ 65 years of age. Of these, 1,081 patients (14%) were between the ages of 65 and 74 and 864 patients (12%) were 75 years or older. No overall differences in safety or effectiveness were observed between these subjects and younger subjects, but greater sensitivity of some older individuals cannot be ruled out.
Severe, and sometimes fatal, cases of hepatotoxicity have been reported post-marketing in association with levofloxacin. The majority of fatal hepatotoxicity reports occurred in patients 65 years of age or older and most were not associated with hypersensitivity. Levofloxacin should be discontinued immediately if the patient develops signs and symptoms of hepatitis [see Warnings and Precautions (5.8)].
Epidemiologic studies report an increased rate of aortic aneurysm and dissection within two months following use of fluoroquinolones, particularly in elderly patients [see Warnings and Precautions (5.9)].
Elderly patients may be more susceptible to drug-associated effects on the QT interval. Therefore, precaution should be taken when using levofloxacin with concomitant drugs that can result in prolongation of the QT interval (e.g., Class IA or Class III antiarrhythmics) or in patients with risk factors for torsade de pointes (e.g., known QT prolongation, uncorrected hypokalemia) [see Warnings and Precautions (5.11)].
The pharmacokinetic properties of levofloxacin in younger adults and elderly adults do not differ significantly when creatinine clearance is taken into consideration. However, since the drug is known to be substantially excreted by the kidney, the risk of toxic reactions to this drug may be greater in patients with impaired renal function. Because elderly patients are more likely to have decreased renal function, care should be taken in dose selection, and it may be useful to monitor renal function [see Clinical Pharmacology (12.3)].

8.6 Renal Impairment

Clearance of levofloxacin is substantially reduced and plasma elimination half-life is substantially prolonged in patients with renal impairment (creatinine clearance < 50 mL/min), requiring dosage adjustment in such patients to avoid accumulation. Neither hemodialysis nor continuous ambulatory peritoneal dialysis (CAPD) is effective in removal of levofloxacin from the body, indicating that supplemental doses of levofloxacin are not required following hemodialysis or CAPD [see Dosage and Administration (2.3)].

8.7 Hepatic Impairment

Pharmacokinetic studies in patients with hepatic impairment have not been conducted. Due to the limited extent of levofloxacin metabolism, the pharmacokinetics of levofloxacin are not expected to be affected by hepatic impairment.

10 OVERDOSAGE

In the event of an acute overdosage, the stomach should be emptied. The patient should be observed and appropriate hydration maintained. Levofloxacin is not efficiently removed by hemodialysis or peritoneal dialysis.
Levofloxacin exhibits a low potential for acute toxicity. Mice, rats, dogs and monkeys exhibited the following clinical signs after receiving a single high dose of levofloxacin: ataxia, ptosis, decreased locomotor activity, dyspnea, prostration, tremors, and convulsions. Doses in excess of 1500 mg/kg orally (approximately 10 or 19 times MRHD in mice and rats, respectively) and 250 mg/kg IV produced significant mortality (estimated to be greater than or equal to 50%) in rodents.

11 DESCRIPTION

Levofloxacin tablets, USP are synthetic antibacterial agents for oral administration. Chemically, levofloxacin, a chiral fluorinated carboxyquinolone, is the pure (-)-(S)-enantiomer of the racemic drug substance ofloxacin. The chemical name is (-)-(S)-9-fluoro-2,3-dihydro-3-methyl-10-(4-methyl-1-piperazinyl)-7-oxo-7H-pyrido [1,2,3-de]-1,4-benzoxazine-6-carboxylic acid hemihydrate.
Figure 1: The Chemical Structure of Levofloxacin, USP

The molecular formula is C18H20FN3O4• 1⁄2 H2O and the molecular weight is 370.38. Levofloxacin, USP is a light yellowish-white to yellow-white crystals or crystalline powder. The molecule exists as a zwitterion at the pH conditions in the small intestine.
The data demonstrate that from pH 0.6 to 5.8, the solubility of levofloxacin, USP is essentially constant (approximately 100 mg/mL). Levofloxacin, USP is considered soluble to freely solublein this pH range, as defined by USP nomenclature. Above pH 5.8, the solubility increases rapidly to its maximum at pH 6.7 (272 mg/mL) and is considered freely solublein this range. Above pH 6.7, the solubility decreases and reaches a minimum value (about 50 mg/mL) at a pH of approximately 6.9.
Levofloxacin, USP has the potential to form stable coordination compounds with many metal ions. This in vitrochelation potential has the following formation order: Al^+3>Cu^+2>Zn^+2>Mg^+2>Ca^+2.
Levofloxacin Tablets, USP are available as film-coated tablets and contain the following inactive ingredients:
• 250 mg: croscarmellose sodium, hypromellose, iron oxide red, magnesium stearate, microcrystalline cellulose, polyethylene glycol, polysorbate 80, povidone and titanium dioxide.
• 500 mg: croscarmellose sodium, hypromellose, iron oxide red, iron oxide yellow, magnesium stearate, microcrystalline cellulose, polyethylene glycol, polysorbate 80, povidone and titanium dioxide.
• 750 mg: croscarmellose sodium, hypromellose, magnesium stearate, microcrystalline cellulose, polyethylene glycol, polysorbate 80, povidone and titanium dioxide.
Levofloxacin tablets, USP meets USP Dissolution Test 2.

12 CLINICAL PHARMACOLOGY

12.1 Mechanism of Action

Levofloxacin is a member of the fluoroquinolone class of antibacterial agents [see Microbiology (12.4)].

12.3 Pharmacokinetics

The mean ± SD pharmacokinetic parameters of levofloxacin determined under single and steady-state conditions following administration of the oral tablets, are summarized in Table 8.
Table 8: Mean ± SD Levofloxacin PK Parameters

Regimen | Cmax (mcg/mL) | Tmax (h) | AUC (mcg•h/mL) | CL/F^1(mL/min) | Vd/F^2(L) | t1/2 (h) | CLR(mL/min)
Single dose
250 mg oral tablet^3 | 2.8 ± 0.4 | 1.6 ± 1.0 | 27.2 ± 3.9 | 156 ± 20 | ND | 7.3 ± 0.9 | 142 ± 21
500 mg oral tablet^3* | 5.1 ± 0.8 | 1.3 ± 0.6 | 47.9 ± 6.8 | 178 ± 28 | ND | 6.3 ± 0.6 | 103 ± 30
750 mg oral tablet^4* | 9.3 ± 1.6 | 1.6 ± 0.8 | 101 ± 20 | 129 ± 24 | 83 ± 17 | 7.5 ± 0.9 | ND
Multiple dose
500 mg every 24h oral tablet^3 | 5.7 ± 1.4 | 1.1 ± 0.4 | 47.5 ± 6.7 | 175 ± 25 | 102 ± 22 | 7.6 ± 1.6 | 116 ± 31
750 mg every 24h oral tablet^4 | 8.6 ± 1.9 | 1.4 ± 0.5 | 90.7 ± 17.6 | 143 ± 29 | 100 ± 16 | 8.8 ± 1.5 | 116 ± 28
500 mg oral tablet single dose, effects of gender and age:
Male^5 | 5.5 ± 1.1 | 1.2 ± 0.4 | 54.4 ± 18.9 | 166 ± 44 | 89 ± 13 | 7.5 ± 2.1 | 126 ± 38
Female^6 | 7.0 ± 1.6 | 1.7 ± 0.5 | 67.7 ± 24.2 | 136 ± 44 | 62 ± 16 | 6.1 ± 0.8 | 106 ± 40
Young^7 | 5.5 ± 1.0 | 1.5 ± 0.6 | 47.5 ± 9.8 | 182 ± 35 | 83 ± 18 | 6.0 ± 0.9 | 140 ± 33
Elderly^8 | 7.0 ± 1.6 | 1.4 ± 0.5 | 74.7 ± 23.3 | 121 ± 33 | 67 ± 19 | 7.6 ± 2.0 | 91 ± 29
500 mg oral single dose tablet, patients with renal impairment:
CLCR 50-80 mL/min | 7.5 ± 1.8 | 1.5 ± 0.5 | 95.6 ± 11.8 | 88 ± 10 | ND | 9.1 ± 0.9 | 57 ± 8
CLCR 20-49 mL/min | 7.1 ± 3.1 | 2.1 ± 1.3 | 182.1 ± 62.6 | 51 ± 19 | ND | 27 ± 10 | 26 ± 13
CLCR <20 mL/min | 8.2 ± 2.6 | 1.1 ± 1.0 | 263.5 ± 72.5 | 33 ± 8 | ND | 35 ± 5 | 13 ± 3
Hemodialysis | 5.7 ± 1.0 | 2.8 ± 2.2 | ND | ND | ND | 76 ± 42 | ND
CAPD | 6.9 ± 2.3 | 1.4 ± 1.1 | ND | ND | ND | 51 ± 24 | ND

^1clearance/bioavailability
^2volume of distribution/bioavailability
^3healthy males 18 to 53 years of age
^4healthy male and female subjects 18 to 54 years of age
^5healthy males 22 to 75 years of age
^6healthy females 18 to 80 years of age
^7young healthy male and female subjects 18 to 36 years of age
^8healthy elderly male and female subjects 66 to 80 years of age
* Absolute bioavailability; F=0.99 ± 0.08 from a 500 mg tablet and F=0.99 ± 0.06 from a 750 mg tablet;
ND=not determined.
Levofloxacin pharmacokinetics are linear and predictable after single and multiple oral or IV dosing regimens. Steady-state conditions are reached within 48 hours following a 500 mg or 750 mg once-daily dosage regimen. The mean ± SD peak and trough plasma concentrations attained following multiple once-daily oral dosage regimens were approximately 5.7 ± 1.4 and 0.5 ± 0.2 mcg/mL after the 500 mg doses, and 8.6 ± 1.9 and 1.1 ± 0.4 mcg/mL after the 750 mg doses, respectively. The mean ± SD peak and trough plasma concentrations attained following multiple once-daily IV regimens were approximately 6.4 ± 0.8 and 0.6 ± 0.2 mcg/mL after the 500 mg doses, and 12.1 ± 4.1 and 1.3 ± 0.71 mcg/mL after the 750 mg doses, respectively.
Absorption
Levofloxacin is rapidly and essentially completely absorbed after oral administration. Peak plasma concentrations are usually attained one to two hours after oral dosing. The absolute bioavailability of levofloxacin from a 500 mg tablet and a 750 mg tablet of levofloxacin are both approximately 99%, demonstrating complete oral absorption of levofloxacin. Following a single intravenous dose of levofloxacin to healthy volunteers, the mean ± SD peak plasma concentration attained was 6.2 ± 1 mcg/mL after a 500 mg dose infused over 60 minutes and 11.5 ± 4 mcg/mL after a 750 mg dose infused over 90 minutes. Oral administration of a 500 mg dose levofloxacin with food prolongs the time to peak concentration by approximately 1 hour and decreases the peak concentration by approximately 14% following tablet and approximately 25% following oral solution administration. Therefore, levofloxacin tablets can be administered without regard to food.
The plasma concentration profile of levofloxacin after IV administration is similar and comparable in extent of exposure (AUC) to that observed for levofloxacin tablets when equal doses (mg/mg) are administered. Therefore, the oral and IV routes of administration can be considered interchangeable.
Distribution
The mean volume of distribution of levofloxacin generally ranges from 74 to 112 L after single and multiple 500 mg or 750 mg doses, indicating widespread distribution into body tissues. Levofloxacin reaches its peak levels in skin tissues and in blister fluid of healthy subjects at approximately 3 hours after dosing. The skin tissue biopsy to plasma AUC ratio is approximately 2 and the blister fluid to plasma AUC ratio is approximately 1 following multiple once-daily oral administration of 750 mg and 500 mg doses of levofloxacin, respectively, to healthy subjects. Levofloxacin also penetrates well into lung tissues. Lung tissue concentrations were generally 2- to 5-fold higher than plasma concentrations and ranged from approximately 2.4 to 11.3 mcg/g over a 24-hour period after a single 500 mg oral dose.
In vitro, over a clinically relevant range (1 to 10 mcg/mL) of serum/plasma levofloxacin concentrations, levofloxacin is approximately 24 to 38% bound to serum proteins across all species studied, as determined by the equilibrium dialysis method. Levofloxacin is mainly bound to serum albumin in humans. Levofloxacin binding to serum proteins is independent of the drug concentration.
Elimination
Metabolism
Levofloxacin is stereochemically stable in plasma and urine and does not invert metabolically to its enantiomer, D-ofloxacin. Levofloxacin undergoes limited metabolism in humans and is primarily excreted as unchanged drug in the urine. Following oral administration, approximately 87% of an administered dose was recovered as unchanged drug in urine within 48 hours, whereas less than 4% of the dose was recovered in feces in 72 hours. Less than 5% of an administered dose was recovered in the urine as the desmethyl and N-oxide metabolites, the only metabolites identified in humans. These metabolites have little relevant pharmacological activity.
Excretion
Levofloxacin is excreted largely as unchanged drug in the urine. The mean terminal plasma elimination half-life of levofloxacin ranges from approximately 6 to 8 hours following single or multiple doses of levofloxacin given orally or intravenously. The mean apparent total body clearance and renal clearance range from approximately 144 to 226 mL/min and 96 to 142 mL/min, respectively. Renal clearance in excess of the glomerular filtration rate suggests that tubular secretion of levofloxacin occurs in addition to its glomerular filtration. Concomitant administration of either cimetidine or probenecid results in approximately 24% and 35% reduction in the levofloxacin renal clearance, respectively, indicating that secretion of levofloxacin occurs in the renal proximal tubule. No levofloxacin crystals were found in any of the urine samples freshly collected from subjects receiving levofloxacin.
Specific Populations
Geriatric Patients
There are no significant differences in levofloxacin pharmacokinetics between young and elderly subjects when the subjects’ differences in creatinine clearance are taken into consideration. Following a 500 mg oral dose of levofloxacin to healthy elderly subjects (66 to 80 years of age), the mean terminal plasma elimination half-life of levofloxacin was about 7.6 hours, as compared to approximately 6 hours in younger adults. The difference was attributable to the variation in renal function status of the subjects and was not believed to be clinically significant. Drug absorption appears to be unaffected by age. Levofloxacin dose adjustment based on age alone is not necessary [see Use in Specific Populations (8.5)].
Pediatric Patients
The pharmacokinetics of levofloxacin following a single 7 mg/kg intravenous dose were investigated in pediatric patients ranging in age from 6 months to 16 years. Pediatric patients cleared levofloxacin faster than adult patients, resulting in lower plasma exposures than adults for a given mg/kg dose. Subsequent pharmacokinetic analyses predicted that a dosage regimen of 8 mg/kg every 12 hours (not to exceed 250 mg per dose) for pediatric patients 6 months to 17 years of age would achieve comparable steady state plasma exposures (AUC0 to 24and Cmax) to those observed in adult patients administered 500 mg of levofloxacin once every 24 hours. Levofloxacin Tablets can only be administered to pediatric patients with inhalational anthrax (post-exposure) or plague who are 30 kg or greater due to the limitations of the available strengths [see Dosage and Administration (2.2)]
Male and Female Subjects
There are no significant differences in levofloxacin pharmacokinetics between male and female subjects when subjects’ differences in creatinine clearance are taken into consideration. Following a 500 mg oral dose of levofloxacin to healthy male subjects, the mean terminal plasma elimination half-life of levofloxacin was about 7.5 hours, as compared to approximately 6.1 hours in female subjects. This difference was attributable to the variation in renal function status of the male and female subjects and was not believed to be clinically significant. Drug absorption appears to be unaffected by the gender of the subjects. Dose adjustment based on gender alone is not necessary.
Racial or Ethnic Groups
The effect of race on levofloxacin pharmacokinetics was examined through a covariate analysis performed on data from 72 subjects: 48 white and 24 non-white. The apparent total body clearance and apparent volume of distribution were not affected by the race of the subjects.
Patients with Renal Impairment
Clearance of levofloxacin is substantially reduced and plasma elimination half-life is substantially prolonged in adult patients with impaired renal function (creatinine clearance < 50 mL/min), requiring dosage adjustment in such patients to avoid accumulation. Neither hemodialysis nor continuous ambulatory peritoneal dialysis (CAPD) is effective in removal of levofloxacin from the body, indicating that supplemental doses of levofloxacin are not required following hemodialysis or CAPD [see Dosage and Administration (2.3)and Use in Specific Populations (8.6)].
Patients with Hepatic Impairment
Pharmacokinetic studies in hepatically impaired patients have not been conducted. Due to the limited extent of levofloxacin metabolism, the pharmacokinetics of levofloxacin are not expected to be affected by hepatic impairment [see Use in Specific Populations (8.7)].
Patients with Bacterial Infection
The pharmacokinetics of levofloxacin in patients with serious community-acquired bacterial infections are comparable to those observed in healthy subjects.
Drug Interaction Studies
The potential for pharmacokinetic drug interactions between levofloxacin and antacids, warfarin, theophylline, cyclosporine, digoxin, probenecid, and cimetidine has been evaluated [see Drug Interactions (7)].

12.4 Microbiology

Mechanism of Action
Levofloxacin is the L-isomer of the racemate, ofloxacin, a quinolone antimicrobial agent. The antibacterial activity of ofloxacin resides primarily in the L-isomer. The mechanism of action of levofloxacin and other fluoroquinolone antimicrobials involves inhibition of bacterial topoisomerase IV and DNA gyrase (both of which are type II topoisomerases), enzymes required for DNA replication, transcription, repair and recombination.
Resistance
Fluoroquinolone resistance can arise through mutations in defined regions of DNA gyrase or topoisomerase IV, termed the Quinolone-Resistance Determining Regions (QRDRs), or through altered efflux.
Fluoroquinolones, including levofloxacin, differ in chemical structure and mode of action from aminoglycosides, macrolides and β-lactam antibiotics, including penicillins. Fluoroquinolones may, therefore, be active against bacteria resistant to these antimicrobials.
Resistance to levofloxacin due to spontaneous mutation in vitrois a rare occurrence (range: 10^-9to 10^-10). Cross-resistance has been observed between levofloxacin and some other fluoroquinolones, some microorganisms resistant to other fluoroquinolones may be susceptible to levofloxacin.
Antimicrobial Activity
Levofloxacin has in vitroactivity against Gram-negative and Gram-positive bacteria.
Levofloxacin has been shown to be active against most isolates of the following bacteria both in vitro and in clinical infections as described in Indications and Usage (1):
Aerobic bacteria
Gram-Positive Bacteria
Enterococcus faecalis
Staphylococcus aureus (methicillin-susceptible isolates)
Staphylococcus epidermidis (methicillin-susceptible isolates)
Staphylococcus saprophyticus
Streptococcus pneumoniae (including multi-drug resistant isolates [MDRSP]^1)
Streptococcus pyogenes
Gram-Negative Bacteria
Enterobacter cloacae
^1MDRSP (Multi-drug resistant Streptococcus pneumoniae)

isolates are isolates resistant to two or more of the following antibiotics: penicillin (MIC ≥2 mcg/mL), 2ndgeneration cephalosporins, e.g., cefuroxime; macrolides, tetracyclines and trimethoprim/sulfamethoxazole.

Escherichia coli
Haemophilus influenzae
Haemophilus parainfluenzae
Klebsiella pneumoniae
Legionella pneumophila
Moraxella catarrhalis
Proteus mirabilis
Pseudomonas aeruginosa
Serratia marcescens
Other microorganisms
Chlamydophila pneumoniae
Mycoplasma pneumoniae
The following in vitrodata are available, but their clinical significance is unknown. At least 90 percent of the following bacteria exhibit an in vitrominimum inhibitory concentrations (MIC) less than or equal to the susceptible breakpoint for levofloxacin against isolates of similar genus or organism group. However, efficacy of levofloxacin in treating clinical infections caused by these bacteria has not been established in adequate and well-controlled clinical trials.
Aerobic bacteria
Gram-Positive Bacteria
Staphylococcus haemolyticus
β-hemolytic Streptococcus (Group C/F)
β-hemolytic Streptococcus (Group G)
Streptococcus agalactiae
Streptococcus milleri
Viridans group streptococci
Bacillus anthracis
Gram-Negative Bacteria
Acinetobacter baumannii
Acinetobacter lwoffii
Bordetella pertussis
Citrobacter koseri
Citrobacter freundii
Enterobacter aerogenes
Enterobacter sakazakii
Klebsiella oxytoca
Morganella morganii
Pantoea agglomerans
Proteus vulgaris
Providencia rettgeri
Providencia stuartii
Pseudomonas fluorescens
Yersinia pestis
Anaerobic bacteria
Gram-Positive Bacteria
Clostridium perfringens
Susceptibility Tests
For specific information regarding susceptibility test interpretive criteria and associated test methods and quality control standards recognized by FDA for this drug, please see: https://www.fda.gov/STIC.

13 NONCLINICAL TOXICOLOGY

13.1 Carcinogenesis, Mutagenesis, Impairment of Fertility

In a lifetime bioassay in rats, levofloxacin exhibited no carcinogenic potential following daily dietary administration for 2 years; the highest dose (100 mg/kg/day) was 1.4 times the Maximum Recommended Human Dose (MRHD) (750 mg) after normalization for total body surface area. Levofloxacin did not shorten the time to tumor development of UV-induced skin tumors in hairless albino (Skh-1) mice at any levofloxacin dose level and was therefore not photo-carcinogenic under conditions of this study. Dermal levofloxacin concentrations in the hairless mice ranged from 25 to 42 mcg/g at the highest levofloxacin dose level (300 mg/kg/day) used in the photo-carcinogenicity study. By comparison, dermal levofloxacin concentrations in human subjects receiving 750 mg of levofloxacin averaged approximately 11.8 mcg/g at Cmax.
Levofloxacin was not mutagenic in the following assays: Ames bacterial mutation assay (S. typhimuriumand E. coli), CHO/HGPRT forward mutation assay, mouse micronucleus test, mouse dominant lethal test, rat unscheduled DNA synthesis assay, and the mouse sister chromatid exchange assay. It was positive in the in vitrochromosomal aberration (CHL cell line) and sister chromatid exchange (CHL/IU cell line) assays.
Levofloxacin caused no impairment of fertility or reproductive performance in rats at oral doses as high as 360 mg/kg/day, corresponding to 4.2 times the MRHD and intravenous doses as high as 100 mg/kg/day, corresponding to 1.2 times the MRHD after normalization for total body surface area.

13.2 Animal Toxicology and/or Pharmacology

Levofloxacin and other quinolones have been shown to cause arthropathy in immature animals of most species tested [see Warnings and Precautions (5.12)]. In immature dogs (4 to 5 months old), oral doses of 10 mg/kg/day for 7 days and intravenous doses of 4 mg/kg/day for 14 days of levofloxacin resulted in arthropathic lesions. Administration at oral doses of 300 mg/kg/day for 7 days and intravenous doses of 60 mg/kg/day for 4 weeks produced arthropathy in juvenile rats. Three-month old beagle dogs dosed orally with levofloxacin at 40 mg/kg/day exhibited clinically severe arthrotoxicity resulting in the termination of dosing at Day 8 of a 14-day dosing routine (dosing was terminated in the low and mid-dose groups on Day 9 due to similar findings at the mid-dose). Slight musculoskeletal clinical effects, in the absence of gross pathological or histopathological effects, resulted from the lowest dose level of 2.5 mg/kg/day (approximately 0.2-fold the pediatric dose based upon AUC comparisons). Synovitis and articular cartilage lesions were observed at the 10 and 40 mg/kg dose levels (approximately 0.7-fold and 2.4-fold the pediatric dose, respectively, based on AUC comparisons). Articular cartilage gross pathology and histopathology persisted to the end of the 18-week recovery period for those dogs from the 10 and 40 mg/kg/day dose levels. The low and mid-dose groups in that study were also evaluated by electron microscopy, revealing compound-related ultrastructural effects in articular cartilage chondrocytes at the end of treatment and at the end of recovery in both of those doses.
When tested in a mouse ear swelling bioassay, levofloxacin exhibited phototoxicity similar in magnitude to ofloxacin, but less phototoxicity than other quinolones.
While crystalluria has been observed in some intravenous rat studies, urinary crystals are not formed in the bladder, being present only after micturition and are not associated with nephrotoxicity.
In mice, the CNS stimulatory effect of quinolones is enhanced by concomitant administration of non-steroidal anti-inflammatory drugs.
In dogs, levofloxacin administered at 6 mg/kg or higher by rapid intravenous injection produced hypotensive effects. These effects were considered to be related to histamine release.
In vitroand in vivostudies in animals indicate that levofloxacin is neither an enzyme inducer nor inhibitor in the human therapeutic plasma concentration range; therefore, no drug metabolizing enzyme-related interactions with other drugs or agents are anticipated.

14 CLINICAL STUDIES

14.1 Nosocomial Pneumonia

Adult patients with clinically and radiologically documented nosocomial pneumonia were enrolled in a multicenter, randomized, open-label study comparing intravenous levofloxacin (750 mg once daily) followed by oral levofloxacin (750 mg once daily) for a total of 7 to 15 days to intravenous imipenem/cilastatin (500 to 1000 mg every 6 to 8 hours daily) followed by oral ciprofloxacin (750 mg every 12 hours daily) for a total of 7 to 15 days. Levofloxacin-treated patients received an average of 7 days of intravenous therapy (range: 1 to 16 days); comparator-treated patients received an average of 8 days of intravenous therapy (range: 1 to 19 days).
Overall, in the clinically and microbiologically evaluable population, adjunctive therapy was empirically initiated at study entry in 56 of 93 (60.2%) patients in the levofloxacin arm and 53 of 94 (56.4%) patients in the comparator arm. The average duration of adjunctive therapy was 7 days in the levofloxacin arm and 7 days in the comparator. In clinically and microbiologically evaluable patients with documented Pseudomonas aeruginosainfection, 15 of 17 (88.2%) received ceftazidime (N = 11) or piperacillin/tazobactam (N = 4) in the levofloxacin arm and 16 of 17 (94.1%) received an aminoglycoside in the comparator arm. Overall, in clinically and microbiologically evaluable patients, vancomycin was added to the treatment regimen of 37 of 93 (39.8%) patients in the levofloxacin arm and 28 of 94 (29.8%) patients in the comparator arm for suspected methicillin-resistant S. aureusinfection.
Clinical success rates in clinically and microbiologically evaluable patients at the post-therapy visit (primary study endpoint assessed on day 3 to 15 after completing therapy) were 58.1% for levofloxacin and 60.6% for comparator. The 95% CI for the difference of response rates (levofloxacin minus comparator) was [-17.2, 12.0]. The microbiological eradication rates at the posttherapy visit were 66.7% for levofloxacin and 60.6% for comparator. The 95% CI for the difference of eradication rates (levofloxacin minus comparator) was [-8.3, 20.3]. Clinical success and microbiological eradication rates by pathogen are detailed in Table 9.
Table 9: Clinical Success Rates and Bacteriological Eradication Rates (Nosocomial Pneumonia)

Pathogen | N | Levofloxacin No. (%) of Patients Microbiologic/ Clinical Outcomes | N | Imipenem/Cilastatin No. (%) of Patients Microbiologic/ Clinical Outcomes
MSSA* | 21 | 14 (66.7)/13 (61.9) | 19 | 13 (68.4)/15 (78.9)
P. aeruginosa † | 17 | 10 (58.8)/11 (64.7) | 17 | 5 (29.4)/7 (41.2)
S. marcescens | 11 | 9 (81.8)/7 (63.6) | 7 | 2 (28.6)/3 (42.9)
E. coli | 12 | 10 (83.3)/7 (58.3) | 11 | 7 (63.6)/8 (72.7)
K. pneumoniae ‡ | 11 | 9 (81.8)/5 (45.5) | 7 | 6 (85.7)/3 (42.9)
H. influenzae | 16 | 13 (81.3)/10 (62.5) | 15 | 14 (93.3)/11 (73.3)
S. pneumoniae | 4 | 3 (75.0)/3 (75.0) | 7 | 5 (71.4)/4 (57.1)

*Methicillin-susceptible S. aureus
†See above text for use of combination therapy
‡The observed differences in rates for the clinical and microbiological outcomes may reflect other factors that were not accounted for in the study

14.2 Community-Acquired Pneumonia: 7 to 14 day Treatment Regimen

Adult inpatients and outpatients with a diagnosis of community-acquired bacterial pneumonia were evaluated in 2 pivotal clinical studies. In the first study, 590 patients were enrolled in a prospective, multi-center, unblinded randomized trial comparing levofloxacin 500 mg once daily orally or intravenously for 7 to 14 days to ceftriaxone 1 to 2 grams intravenously once or in equally divided doses twice daily followed by cefuroxime axetil 500 mg orally twice daily for a total of 7 to 14 days. Patients assigned to treatment with the control regimen were allowed to receive erythromycin (or doxycycline if intolerant of erythromycin) if an infection due to atypical pathogens was suspected or proven. Clinical and microbiologic evaluations were performed during treatment, 5 to 7 days posttherapy, and 3 to 4 weeks posttherapy. Clinical success (cure plus improvement) with levofloxacin at 5 to 7 days posttherapy, the primary efficacy variable in this study, was superior (95%) to the control group (83%). The 95% CI for the difference of response rates (levofloxacin minus comparator) was [-6, 19]. In the second study, 264 patients were enrolled in a prospective, multi-center, non-comparative trial of 500 mg levofloxacin administered orally or intravenously once daily for 7 to 14 days. Clinical success for clinically evaluable patients was 93%. For both studies, the clinical success rate in patients with atypical pneumonia due to Chlamydophila pneumoniae, Mycoplasma pneumoniae, and Legionella pneumophilawere 96%, 96%, and 70%, respectively. Microbiologic eradication rates across both studies are presented in Table 10.
Table 10: Bacteriological Eradication Rates Across 2 Community Acquired Pneumonia Clinical Studies

Pathogen | No. Pathogens | Bacteriological Eradication Rate (%)
H. influenzae | 55 | 98
S. pneumoniae | 83 | 95
S. aureus | 17 | 88
M. catarrhalis | 18 | 94
H. parainfluenzae | 19 | 95
K. pneumoniae | 10 | 100.0

Community-Acquired Pneumonia Due to Multi-Drug Resistant Streptococcus pneumoniae
Levofloxacin was effective for the treatment of community-acquired pneumonia caused by multi-drug resistant Streptococcus pneumoniae(MDRSP). MDRSP isolates are isolates resistant to two or more of the following antibacterials: penicillin (MIC ≥2 mcg/mL), 2ndgeneration cephalosporins (e.g., cefuroxime, macrolides, tetracyclines and trimethoprim/sulfamethoxazole). Of 40 microbiologically evaluable patients with MDRSP isolates, 38 patients (95%) achieved clinical and bacteriologic success at post-therapy. The clinical and bacterial success rates are shown in Table 11.
Table 11: Clinical and Bacterial Success Rates for Levofloxacin-Treated MDRSP in Community Acquired Pneumonia Patients (Population Valid for Efficacy)

Screening Susceptibility | Clinical Success |  | Bacteriological Success *
Screening Susceptibility | n/N † | % | n/N ‡ | %
Penicillin-resistant | 16/17 | 94.1 | 16/17 | 94.1
2ndgeneration Cephalosporin resistant | 31/32 | 96.9 | 31/32 | 96.9
Macrolide-resistant | 28/29 | 96.6 | 28/29 | 96.6
Trimethoprim/Sulfamethoxazole resistant | 17/19 | 89.5 | 17/19 | 89.5
Tetracycline-resistant | 12/12 | 100 | 12/12 | 100

*One patient had a respiratory isolate that was resistant to tetracycline, cefuroxime, macrolides and TMP/SMX and intermediate to penicillin and a blood isolate that was intermediate to penicillin and cefuroxime and resistant to the other classes. The patient is included in the database based on respiratory isolate.
† n= the number of microbiologically evaluable patients who were clinical successes; N= number of microbiologically evaluable patients in the designated resistance group.
‡ n= the number of MDRSP isolates eradicated or presumed eradicated in microbiologically evaluable patients; N= number of MDRSP isolates in a designated resistance group.
Not all isolates were resistant to all antimicrobial classes tested. Success and eradication rates are summarized in Table 12.
Table 12: Clinical Success and Bacteriologic Eradication Rates for Resistant Streptococcus pneumoniae(Community Acquired Pneumonia)

Type of Resistance | Clinical Success | Bacteriologic Eradication
Resistant to 2 antibacterials | 17/18 (94.4%) | 17/18 (94.4%)
Resistant to 3 antibacterials | 14/15 (93.3%) | 14/15 (93.3%)
Resistant to 4 antibacterials | 7/7 (100%) | 7/7 (100%)
Resistant to 5 antibacterials | 0 | 0
Bacteremia with MDRSP | 8/9 (89%) | 8/9 (89%)

14.3 Community-Acquired Pneumonia: 5-day Treatment Regimen

To evaluate the safety and efficacy of the higher dose and shorter course of levofloxacin, 528 outpatient and hospitalized adults with clinically and radiologically determined mild to severe community-acquired pneumonia were evaluated in a double-blind, randomized, prospective, multicenter study comparing levofloxacin 750 mg, IV or orally, every day for five days or levofloxacin 500 mg IV or orally, every day for 10 days.
Clinical success rates (cure plus improvement) in the clinically evaluable population were 90.9% in the levofloxacin 750 mg group and 91.1% in the levofloxacin 500 mg group. The 95% CI for the difference of response rates (levofloxacin 750 minus levofloxacin 500) was [-5.9, 5.4]. In the clinically evaluable population (31 to 38 days after enrollment) pneumonia was observed in 7 out of 151 patients in the levofloxacin 750 mg group and 2 out of 147 patients in the levofloxacin 500 mg group. Given the small numbers observed, the significance of this finding cannot be determined statistically. The microbiological efficacy of the 5-day regimen was documented for infections listed in Table 13.
Table 13: Bacteriological Eradication Rates (Community-Acquired Pneumonia)

S. pneumoniae | 19/20 (95%)
Haemophilus influenzae | 12/12 (100%)
Haemophilus parainfluenzae | 10/10 (100%)
Mycoplasma pneumoniae | 26/27 (96%)
Chlamydophila pneumoniae | 13/15 (87%)

14.4 Acute Bacterial Sinusitis: 5-day and 10 to 14 day Treatment Regimens

Levofloxacin is approved for the treatment of acute bacterial sinusitis (ABS) using either 750 mg by mouth x 5 days or 500 mg by mouth once daily x 10 to 14 days. To evaluate the safety and efficacy of a high dose short course of levofloxacin, 780 outpatient adults with clinically and radiologically determined acute bacterial sinusitis were evaluated in a double-blind, randomized, prospective, multicenter study comparing levofloxacin 750 mg by mouth once daily for five days to levofloxacin 500 mg by mouth once daily for 10 days.
Clinical success rates (defined as complete or partial resolution of the pre-treatment signs and symptoms of ABS to such an extent that no further antibiotic treatment was deemed necessary) in the microbiologically evaluable population were 91.4% (139/152) in the levofloxacin 750 mg group and 88.6% (132/149) in the levofloxacin 500 mg group at the test-of-cure (TOC) visit (95% CI [-4.2, 10.0] for levofloxacin 750 mg minus levofloxacin 500 mg).
Rates of clinical success by pathogen in the microbiologically evaluable population who had specimens obtained by antral tap at study entry showed comparable results for the five- and ten-day regimens at the test-of-cure visit 22 days post treatment (see Table 14).
Table 14: Clinical Success Rate by Pathogen at the TOC in Microbiologically Evaluable Subjects Who Underwent Antral Puncture (Acute Bacterial Sinusitis)

Pathogen | Levofloxacin 750 mg x 5 days | Levofloxacin 500 mg x 10 days
Streptococcus pneumoniae * | 25/27 (92.6%) | 26/27 (96.3%)
Haemophilus influenzae * | 19/21 (90.5%) | 25/27 (92.6%)
Moraxella catarrhalis * | 10/11 (90.9%) | 13/13 (100%)

*Note: Forty percent of the subjects in this trial had specimens obtained by sinus endoscopy. The efficacy data for subjects whose specimen was obtained endoscopically were comparable to those presented in the above table.

14.5 Complicated Skin and Skin Structure Infections

Three hundred ninety-nine patients were enrolled in an open-label, randomized, comparative study for complicated skin and skin structure infections. The patients were randomized to receive either levofloxacin 750 mg once daily (IV followed by oral), or an approved comparator for a median of 10 ± 4.7 days. As is expected in complicated skin and skin structure infections, surgical procedures were performed in the levofloxacin and comparator groups. Surgery (incision and drainage or debridement) was performed on 45% of the levofloxacin-treated patients and 44% of the comparator-treated patients, either shortly before or during antibiotic treatment and formed an integral part of therapy for this indication.
Among those who could be evaluated clinically 2 to 5 days after completion of study drug, overall success rates (improved or cured) were 116/138 (84.1%) for patients treated with levofloxacin and 106/132 (80.3%) for patients treated with the comparator.
Success rates varied with the type of diagnosis ranging from 68% in patients with infected ulcers to 90% in patients with infected wounds and abscesses. These rates were equivalent to those seen with comparator drugs.

14.6 Chronic Bacterial Prostatitis

Adult patients with a clinical diagnosis of prostatitis and microbiological culture results from urine sample collected after prostatic massage (VB3) or expressed prostatic secretion (EPS) specimens obtained via the Meares-Stamey procedure were enrolled in a multicenter, randomized, double-blind study comparing oral levofloxacin 500 mg, once daily for a total of 28 days to oral ciprofloxacin 500 mg, twice daily for a total of 28 days. The primary efficacy endpoint was microbiologic efficacy in microbiologically evaluable patients. A total of 136 and 125 microbiologically evaluable patients were enrolled in the levofloxacin and ciprofloxacin groups, respectively. The microbiologic eradication rate by patient infection at 5 to 18 days after completion of therapy was 75.0% in the levofloxacin group and 76.8% in the ciprofloxacin group (95% CI [-12.58, 8.98] for levofloxacin minus ciprofloxacin). The overall eradication rates for pathogens of interest are presented in Table 15.
Table 15: Bacteriological Eradication Rates (Chronic Bacterial Prostatitis)

 | Levofloxacin (N=136) |  | Ciprofloxacin (N=125)
Pathogen | N | Eradication | N | Eradication
E. coli | 15 | 14 (93.3%) | 11 | 9 (81.8%)
E. faecalis | 54 | 39 (72.2%) | 44 | 33 (75.0%)
S. epidermidis* | 11 | 9 (81.8%) | 14 | 11 (78.6%)

*Eradication rates shown are for patients who had a sole pathogen only; mixed cultures were excluded.
Eradication rates for S. epidermidiswhen found with other co-pathogens are consistent with rates seen in pure isolates.
Clinical success (cure + improvement with no need for further antibiotic therapy) rates in microbiologically evaluable population 5 to 18 days after completion of therapy were 75.0% for levofloxacin-treated patients and 72.8% for ciprofloxacin-treated patients (95% CI [-8.87, 13.27] for levofloxacin minus ciprofloxacin). Clinical long-term success (24 to 45 days after completion of therapy) rates were 66.7% for the levofloxacin-treated patients and 76.9% for the ciprofloxacin-treated patients (95% CI [-23.40, 2.89] for levofloxacin minus ciprofloxacin).

14.7 Complicated Urinary Tract Infections and Acute Pyelonephritis: 5-day Treatment Regimen

To evaluate the safety and efficacy of the higher dose and shorter course of levofloxacin, 1,109 patients with cUTI and AP were enrolled in a randomized, double-blind, multicenter clinical trial conducted in the US from November 2004 to April 2006 comparing levofloxacin 750 mg IV or orally once daily for 5 days (546 patients) with ciprofloxacin 400 mg IV or 500 mg orally twice daily for 10 days (563 patients). Patients with AP complicated by underlying renal diseases or conditions such as complete obstruction, surgery, transplantation, concurrent infection or congenital malformation were excluded. Efficacy was measured by bacteriologic eradication of the baseline organism(s) at the post-therapy visit in patients with a pathogen identified at baseline. The post-therapy (test-of-cure) visit occurred 10 to 14 days after the last active dose of levofloxacin and 5 to 9 days after the last dose of active ciprofloxacin.
The bacteriologic cure rates overall for levofloxacin and control at the test-of-cure (TOC) visit for the group of all patients with a documented pathogen at baseline (modified intent to treat or mITT) and the group of patients in the mITT population who closely followed the protocol (Microbiologically Evaluable) are summarized in Table 16.
Table 16: Bacteriological Eradication at Test-of-Cure

 | Levofloxacin 750 mg orally or IV once daily for 5 days |  | Ciprofloxacin 400 mg IV/500 mg orally twice daily for 10 days |  | Overall Difference [95% CI]
 | n/N | % | n/N | % | Levofloxacin- Ciprofloxacin
mITT Population *
Overall (cUTI or AP) | 252/333 | 75.7 | 239/318 | 75.2 | 0.5 (-6.1, 7.1)
cUTI | 168/230 | 73.0 | 157/213 | 73.7
AP | 84/103 | 81.6 | 82/105 | 78.1
Microbiologically Evaluable Population †
Overall (cUTI or AP) | 228/265 | 86 | 215/241 | 89.2 | -3.2 [-8.9, 2.5]
cUTI | 154/185 | 83.2 | 144/165 | 87.3
AP | 74/80 | 92.5 | 71/76 | 93.4

*The mITT population included patients who received study medication and who had a positive (≥10^5 CFU/mL) urine culture with no more than 2 uropathogens at baseline. Patients with missing response were counted as failures in this analysis.
† The Microbiologically Evaluable population included patients with a confirmed diagnosis of cUTI or AP, a causative organism(s) at baseline present at ≥10^5CFU/mL, a valid test-of-cure urine culture, no pathogen isolated from blood resistant to study drug, no premature discontinuation or loss to follow-up, and compliance with treatment (among other criteria).
Microbiologic eradication rates in the Microbiologically Evaluable population at TOC for individual pathogens recovered from patients randomized to levofloxacin treatment are presented in Table 17.
Table 17: Bacteriological Eradication Rates for Individual Pathogens Recovered From Patients Randomized to Levofloxacin 750 mg QD for 5 Days Treatment

Pathogen | Bacteriological Eradication Rate (n/N) | %
Escherichia coli * | 155/172 | 90
Klebsiella pneumoniae | 20/23 | 87
Proteus mirabilis | 12/12 | 100

*The predominant organism isolated from patients with AP was E. coli: 91% (63/69) eradication in AP and 89% (92/103) in patients with cUTI.

14.8 Complicated Urinary Tract Infections and Acute Pyelonephritis: 10-day Treatment Regimen

To evaluate the safety and efficacy of the 250 mg dose, 10 day regimen of levofloxacin, 567 patients with uncomplicated UTI, mild-to-moderate cUTI, and mild-to-moderate AP were enrolled in a randomized, double-blind, multicenter clinical trial conducted in the US from June 1993 to January 1995 comparing levofloxacin 250 mg orally once daily for 10 days (285 patients) with ciprofloxacin 500 mg orally twice daily for 10 days (282 patients). Patients with a resistant pathogen, recurrent UTI, women over age 55 years, and with an indwelling catheter were initially excluded, prior to protocol amendment which took place after 30% of enrollment. Microbiological efficacy was measured by bacteriologic eradication of the baseline organism(s) at 1 to 12 days post-therapy in patients with a pathogen identified at baseline.
The bacteriologic cure rates overall for levofloxacin and control at the test-of-cure (TOC) visit for the group of all patients with a documented pathogen at baseline (modified intent to treat or mITT) and the group of patients in the mITT population who closely followed the protocol (Microbiologically Evaluable) are summarized in Table 18.
Table 18: Bacteriological Eradication Overall (cUTI or AP) at Test-Of-Cure*

 | Levofloxacin 250 mg once daily for 10 days |  | Ciprofloxacin 500 mg twice daily for 10 days
 | n/N | % | n/N | %
mITT Population † | 174/209 | 83.3 | 184/219 | 84.0
Microbiologically Evaluable Population ‡ | 164/177 | 92.7 | 159/171 | 93.0

*1 to 9 days posttherapy for 30% of subjects enrolled prior to a protocol amendment; 5 to 12 days posttherapy for 70% of subjects.
†The mITT population included patients who had a pathogen isolated at baseline. Patients with missing response were counted as failures in this analysis.
‡ The Microbiologically Evaluable population included mITT patients who met protocol-specified evaluability criteria.

14.9 Inhalational Anthrax (Post-Exposure)

The effectiveness of levofloxacin for this indication is based on plasma concentrations achieved in humans, a surrogate endpoint reasonably likely to predict clinical benefit. Levofloxacin has not been tested in humans for the post-exposure prevention of inhalation anthrax. The mean plasma concentrations of levofloxacin associated with a statistically significant improvement in survival over placebo in the rhesus monkey model of inhalational anthrax are reached or exceeded in adult and pediatric patients receiving the recommended oral and intravenous dosage regimens [see Indications and Usage (1.13) and Dosage and Administration (2.1, 2.2)].
Levofloxacin pharmacokinetics have been evaluated in adult and pediatric patients. The mean (± SD) steady state peak plasma concentration in human adults receiving 500 mg orally or intravenously once daily is 5.7 ± 1.4 and 6.4 ± 0.8 mcg/mL, respectively; and the corresponding total plasma exposure (AUC0 to 24) is 47.5 ± 6.7 and 54.6 ± 11.1 mcg.h/mL, respectively. The predicted steady-state pharmacokinetic parameters in pediatric patients ranging in age from 6 months to 17 years receiving 8 mg/kg orally every 12 hours (not to exceed 250 mg per dose) were calculated to be comparable to those observed in adults receiving 500 mg orally once daily [see Clinical Pharmacology (12.3)] . Levofloxacin tablets can only be administered to pediatric patients with inhalational anthrax (post-exposure) or plague who are 30 kg or greater due to the limitations of the available strengths [see Dosage and Administration (2.2)].
In adults, the safety of levofloxacin for treatment durations of up to 28 days is well characterized. However, information pertaining to extended use at 500 mg daily up to 60 days is limited. Prolonged levofloxacin therapy in adults should only be used when the benefit outweighs the risk.
In pediatric patients, the safety of levofloxacin for treatment durations of more than 14 days has not been studied. An increased incidence of musculoskeletal adverse events (arthralgia, arthritis, tendinopathy, gait abnormality) compared to controls has been observed in clinical studies with treatment duration of up to 14 days. Long-term safety data, including effects on cartilage, following the administration of levofloxacin to pediatric patients is limited [see Warnings and Precautions (5.12) and Use in Specific Populations (8.4)].
A placebo-controlled animal study in rhesus monkeys exposed to an inhaled mean dose of 49 LD50(~2.7 x 10^6) spores (range 17 to 118 LD50) of B. anthracis(Ames strain) was conducted. The minimal inhibitory concentration (MIC) of levofloxacin for the anthrax strain used in this study was 0.125 mcg/mL. In the animals studied, mean plasma concentrations of levofloxacin achieved at expected Tmax(1 hour post-dose) following oral dosing to steady state ranged from 2.79 to 4.87 mcg/mL. Steady state trough concentrations at 24 hours post-dose ranged from 0.107 to 0.164 mcg/mL. Mean (SD) steady state AUC0 to 24was 33.4 ± 3.2 mcg.h/mL (range 30.4 to 36 mcg.h/mL). Mortality due to anthrax for animals that received a 30 day regimen of oral levofloxacin beginning 24 hrs post exposure was significantly lower (1/10), compared to the placebo group (9/10) [P = 0.0011, 2-sided Fisher’s Exact Test]. The one levofloxacin treated animal that died of anthrax did so following the 30-day drug administration period.

14.10 Plague

Efficacy studies of levofloxacin could not be conducted in humans with pneumonic plague for ethical and feasibility reasons. Therefore, approval of this indication was based on an efficacy study conducted in animals.
The mean plasma concentrations of levofloxacin associated with a statistically significant improvement in survival over placebo in an African green monkey model of pneumonic plague are reached or exceeded in adult and pediatric patients receiving the recommended oral and intravenous dosage regimens [see Indications and Usage (1.14)and Dosage and Administration (2.1), (2.2)].
Levofloxacin pharmacokinetics have been evaluated in adult and pediatric patients. The mean (± SD) steady state peak plasma concentration in human adults receiving 500 mg orally or intravenously once daily is 5.7 ± 1.4 and 6.4 ± 0.8 mcg/mL, respectively; and the corresponding total plasma exposure (AUC0 to 24) is 47.5 ± 6.7 and 54.6 ± 11.1 mcg.h/mL, respectively. The predicted steady-state pharmacokinetic parameters in pediatric patients ranging in age from 6 months to 17 years receiving 8 mg/kg orally every 12 hours (not to exceed 250 mg per dose) were calculated to be comparable to those observed in adults receiving 500 mg orally once daily [see Clinical Pharmacology (12.3)]. Levofloxacin tablets can only be administered to pediatric patients with inhalational anthrax (post-exposure) or plague who are 30 kg or greater due to the limitations of the available strengths [see Dosage and Administration (2.2)].
A placebo-controlled animal study in African green monkeys exposed to an inhaled mean dose of 65 LD50(range 3 to 145 LD50) of Yersinia pestis(CO92 strain) was conducted. The minimal inhibitory concentration (MIC) of levofloxacin for the Y. pestisstrain used in this study was 0.03 mcg/mL. Mean plasma concentrations of levofloxacin achieved at the end of a single 30-min infusion ranged from 2.84 to 3.50 mcg/mL in African green monkeys. Trough concentrations at 24 hours post-dose ranged from <0.03 to 0.06 mcg/mL. Mean (SD) AUC0 to 24was 11.9 (3.1) mcg.h/mL (range 9.50 to 16.86 mcg.h/mL). Animals were randomized to receive either a 10-day regimen of i.v. levofloxacin or placebo beginning within 6 hrs of the onset of telemetered fever (≥ 39°C for more than 1 hour). Mortality in the levofloxacin group was significantly lower (1/17) compared to the placebo group (7/7) [p<0.001, Fisher’s Exact Test; exact 95% confidence interval (-99.9%, -55.5%) for the difference in mortality]. One levofloxacin-treated animal was euthanized on Day 9 post-exposure to Y. pestisdue to a gastric complication; it had a blood culture positive for Y. pestison Day 3 and all subsequent daily blood cultures from Day 4 through Day 7 were negative.

16 HOW SUPPLIED/STORAGE AND HANDLING

Levofloxacin Tablets USP, 750 mg are white colored, capsule shaped, biconvex, film coated tablets debossed with '18' on one side and 'I' on the other side. They are supplied in

NDC: 70518-0968-00

NDC: 70518-0968-01

NDC: 70518-0968-02

NDC: 70518-0968-03

PACKAGING: 30 In 1 BLISTER PACK

PACKAGING: 20 in 1 BLISTER PACK

PACKAGING: 7 in 1 BOTTLE PLASTIC

PACKAGING: 5 in 1 BOTTLE PLASTIC

Store at 20° to 25°C (68° to 77°F) [see USP Controlled Room Temperature].

Repackaged and Distributed By:

Remedy Repack, Inc.

625 Kolter Dr. Suite #4 Indiana, PA 1-724-465-8762

17 PATIENT COUNSELING INFORMATION

Advise the patient to read the FDA-approved patient labeling (Medication Guide).
Serious Adverse Reactions
Advise patients to stop taking levofloxacin if they experience an adverse reaction and to call their healthcare provider for advice on completing the full course of treatment with another antibacterial drug.
Inform patients of the following serious adverse reactions that have been associated with levofloxacin or other fluoroquinolone use:
• Disabling and Potentially Irreversible Serious Adverse Reactions That May Occur Together:Inform patients that disabling and potentially irreversible serious adverse reactions, including tendinitis and tendon rupture, peripheral neuropathies, and central nervous system effects, have been associated with use of levofloxacin and may occur together in the same patient. Inform patients to stop taking levofloxacin immediately if they experience an adverse reaction and to call their healthcare provider.
• Tendinitis and Tendon Rupture:Instruct patients to contact their healthcare provider if they experience pain, swelling, or inflammation of a tendon, or weakness or inability to use one of their joints; rest and refrain from exercise; and discontinue levofloxacin treatment. Symptoms may be irreversible. The risk of severe tendon disorder with fluoroquinolones is higher in older patients usually over 60 years of age, in patients taking corticosteroid drugs, and in patients with kidney, heart or lung transplants.
• Peripheral Neuropathies:Inform patients that peripheral neuropathies have been associated with levofloxacin use, symptoms may occur soon after initiation of therapy and may be irreversible. If symptoms of peripheral neuropathy including pain, burning, tingling, numbness and/or weakness develop, immediately discontinue levofloxacin and tell them to contact their physician.
• Central Nervous System Effects(for example, convulsions, dizziness, lightheadedness, increased intracranial pressure): Inform patients that convulsions have been reported in patients receiving fluoroquinolones, including levofloxacin. Instruct patients to notify their physician before taking this drug if they have a history of convulsions. Inform patients that they should know how they react to levofloxacin before they operate an automobile or machinery or engage in other activities requiring mental alertness and coordination. Instruct patients to notify their physician if persistent headache with or without blurred vision occurs.
• Exacerbation of Myasthenia Gravis:Instruct patients to inform their physician of any history of myasthenia gravis. Instruct patients to notify their physician if they experience any symptoms of muscle weakness, including respiratory difficulties.
• Hypersensitivity Reactions:Inform patients that levofloxacin can cause hypersensitivity reactions, even following a single dose, and to discontinue the drug at the first sign of a skin rash, hives or other skin reactions, a rapid heartbeat, difficulty in swallowing or breathing, any swelling suggesting angioedema (for example, swelling of the lips, tongue, face, tightness of the throat, hoarseness), or other symptoms of an allergic reaction.
• Hepatotoxicity:Inform patients that severe hepatotoxicity (including acute hepatitis and fatal events) has been reported in patients taking levofloxacin. Instruct patients to inform their physician if they experience any signs or symptoms of liver injury including: loss of appetite, nausea, vomiting, fever, weakness, tiredness, right upper quadrant tenderness, itching, yellowing of the skin and eyes, light colored bowel movements or dark colored urine.
• Aortic aneurysm and dissection:Inform patients to seek emergency medical care if they experience sudden chest, stomach, or back pain.
• Diarrhea:Diarrhea is a common problem caused by antibiotics which usually ends when the antibiotic is discontinued. Sometimes after starting treatment with antibiotics, patients can develop watery and bloody stools (with or without stomach cramps and fever) even as late as two or more months after having taken the last dose of the antibiotic. If this occurs, instruct patients to contact their physician as soon as possible.
• Prolongation of the QT Interval:Instruct patients to inform their physician of any personal or family history of QT prolongation or proarrhythmic conditions such as hypokalemia, bradycardia, or recent myocardial ischemia; if they are taking any Class IA (quinidine, procainamide), or Class III (amiodarone, sotalol) antiarrhythmic agents. Instruct patients to notify their physician if they have any symptoms of prolongation of the QT interval, including prolonged heart palpitations or a loss of consciousness.
• Musculoskeletal Disorders in Pediatric Patients: Instruct parents to inform their child’s physician if the child has a history of joint-related problems before taking this drug. Inform parents of pediatric patients to notify their child’s physician of any joint-related problems that occur during or following levofloxacin therapy [see Warnings and Precautions (5.12) and Use in Specific Populations (8.4)].
• Photosensitivity/Phototoxicity:Inform patients that photosensitivity/phototoxicity has been reported in patients receiving fluoroquinolones. Inform patients to minimize or avoid exposure to natural or artificial sunlight (tanning beds or UVA/B treatment) while taking fluoroquinolones. If patients need to be outdoors while using fluoroquinolones, instruct them to wear loose-fitting clothes that protect skin from sun exposure and discuss other sun protection measures with their physician. If a sunburn-like reaction or skin eruption occurs, instruct patients to contact their physician.
• Lactation:Advise a lactating woman that she may pump and discard during treatment with levofloxacin and for an additional 2 days after the last dose. Alternatively, advise a lactating woman that breastfeeding is not recommended during treatment with levofloxacin and for an additional 2 days after the last dose [see Use in Specific Populations (8.2)] .
Antibacterial Resistance
Antibacterial drugs including levofloxacin should only be used to treat bacterial infections. They do not treat viral infections (e.g., the common cold). When levofloxacin is prescribed to treat a bacterial infection, patients should be told that although it is common to feel better early in the course of therapy, the medication should be taken exactly as directed. Skipping doses or not completing the full course of therapy may (1) decrease the effectiveness of the immediate treatment and (2) increase the likelihood that bacteria will develop resistance and will not be treatable by levofloxacin or other antibacterial drugs in the future.
Administration with Food, Fluids, and Concomitant Medications
Patients should be informed that levofloxacin tablets may be taken with or without food. The tablets should be taken at the same time each day.
Patients should drink fluids liberally while taking levofloxacin to avoid formation of a highly concentrated urine and crystal formation in the urine.
Antacids containing magnesium, or aluminum, as well as sucralfate, metal cations such as iron, and multivitamin preparations with zinc or didanosine should be taken at least two hours before or two hours after oral levofloxacin administration.
Drug Interactions with Insulin, Oral Hypoglycemic Agents, and Warfarin
Patients should be informed that if they are diabetic and are being treated with insulin or an oral hypoglycemic agent and a hypoglycemic reaction occurs, they should discontinue levofloxacin and consult a physician.
Patients should be informed that concurrent administration of warfarin and levofloxacin has been associated with increases of the International Normalized Ratio (INR) or prothrombin time and clinical episodes of bleeding. Patients should notify their physician if they are taking warfarin, be monitored for evidence of bleeding, and also have their anticoagulation tests closely monitored while taking warfarin concomitantly.
Plague and Anthrax Studies
Patients given levofloxacin for these conditions should be informed that efficacy studies could not be conducted in humans for ethical and feasibility reasons. Therefore, approval for these conditions was based on efficacy studies conducted in animals.

Repackaged By / Distributed By: RemedyRepack Inc.

625 Kolter Drive, Indiana, PA 15701

(724) 465-8762

SPL MEDGUIDE SECTION

Levofloxacin
(LEE-voe-FLOX-a-sin)
Tablets USP

What is the most important information I should know about levofloxacin tablets?
Levofloxacin tablets, a fluoroquinolone antibiotic, can cause serious side effects. Some of these serious side effects can happen at the same time and could result in death.
If you have any of the following serious side effects while you take levofloxacin tablets, you should stop taking levofloxacin tablets immediately and get medical help right away.
1.Tendon rupture or swelling of the tendon (tendinitis).
• Tendon problems can happen in people of all ages who take levofloxacin tablets. Tendons are tough cords of tissue that connect muscles to bones. Some tendon problems include:
o pain
o swelling
o tears and swelling of tendons including the back of the ankle (Achilles), shoulder, hand, or other tendon sites.
• The risk of getting tendon problems while you take levofloxacin tablets is higher if you:
o are over 60 years of age
o are taking steroids (corticosteroids)
o have had a kidney, heart or lung transplant
• Tendon problems can happen in people who do not have the above risk factors when they take levofloxacin tablets.
• Other reasons that can increase your risk of tendon problems can include:
o physical activity or exercise
o kidney failure
o tendon problems in the past, such as in people with rheumatoid arthritis (RA)
• Stop taking levofloxacin tablets immediately and get medical help right away at the first sign of tendon pain, swelling or inflammation. Avoid exercise and using the affected area.
• The most common area of pain and swelling is the Achilles tendon at the back of your ankle. This can also happen with other tendons. You may need a different antibiotic that is not a fluoroquinolone to treat your infection.
• Tendon rupture can happen while you are taking or after you have finished taking levofloxacin tablets. Tendon ruptures can happen within hours or days of taking levofloxacin tablets and have happened up to several months after people have finished taking their fluoroquinolone.
• Stop taking levofloxacin tablets immediately and get medical help right away if you get any of the following signs or symptoms of a tendon rupture:
o hear or feel a snap or pop in a tendon area
o bruising right after an injury in a tendon area
o unable to move the affected area or bear weight
The tendon problems may be permanent.
2. Changes in sensation and possible nerve damage (Peripheral Neuropathy).
Damage to the nerves in arms, hands, legs, or feet can happen in people who take fluoroquinolones, including levofloxacin tablets. Stop taking levofloxacin tablets immediately and talk to your healthcare provider right away if you get any of the following symptoms of peripheral neuropathy in your arms, hands, legs, or feet:
• pain • numbness
• burning • weakness
• tingling
The nerve damage may be permanent.
3. Central Nervous System (CNS) effects. Mental health problems and seizures have been reported in people who take fluoroquinolone antibacterial medicines, including levofloxacin tablets. Tell your healthcare provider if you have a history of mental health problems, including depression, or have a history of seizures before you start taking levofloxacin tablets. CNS side effects may happen as soon as after taking the first dose of levofloxacin tablets. Stop taking levofloxacin tablets immediately and talk to your healthcare provider right away if you get any of these side effects, or other changes in mood or behavior:
• seizures • trouble sleeping
• hear voices, see things, or sense • nightmares
things that are not there (hallucinations)
• feel restless or agitated • feel lightheaded or dizzy
• tremors • feel more suspicious (paranoia)
• feel anxious or nervous • suicidal thoughts or acts
• confusion • headaches that will not go away, with or without blurred vision
• depression • memory problems
• reduced awareness of surroundings • false or strange thoughts or beliefs (delusions)
(delusions) The CNS changes may be permanent.
4. Worsening of myasthenia gravis (a problem that causes muscle weakness).
Fluoroquinolones like levofloxacin tablets may cause worsening of myasthenia gravis symptoms, including muscle weakness and breathing problems. Tell your healthcare provider if you have a history of myasthenia gravis before you start taking levofloxacin tablets. Call your healthcare provider right away if you have any worsening muscle weakness or breathing problems.

What are levofloxacin tablets?
Levofloxacin tablets are a fluoroquinolone antibiotic medicine used in adults age 18 years or older to treat certain infections caused by certain germs called bacteria. These bacterial infections include:
• nosocomial pneumonia • plague
• community acquired pneumonia • urinary tract infections, complicated and uncomplicated
• skin infections, complicated and uncomplicated • acute kidney infection (pyelonephritis)
• chronic prostate infection • acute worsening or chronic bronchitis
• inhalation anthrax germs • acute sinus infection
Studies of levofloxacin tablets for use in the treatment of plague and anthrax were done in animals only, because plague and anthrax could not be studied in people.
Levofloxacin tablets should not be used in people with uncomplicated urinary tract infections, acute bacterial exacerbation of chronic bronchitis, or acute bacterial sinusitis if there are other treatment options available.
Levofloxacin tablets are also used to treat children who weigh at least 66 pounds (or at least 30 kilograms) and may have breathed in anthrax germs, have plague, or been exposed to plague germs.
It is not known if levofloxacin tablets are safe and effective in children under 6 months of age.
The safety and effectiveness in children treated with levofloxacin tablets for more than 14 days is not known.

Who should not take levofloxacin tablets?
Do not take levofloxacin tablets if you have ever had a severe allergic reaction to an antibiotic known as a fluoroquinolone, or if you are allergic to levofloxacin or any of the ingredients in levofloxacin tablets. See the end of this leaflet for a complete list of ingredients in levofloxacin tablets.

Before you take levofloxacin tablets, tell your healthcare provider about all of your medical conditions, including if you:
• have tendon problems. Levofloxacin tablets should not be used in people who have a history of tendon problems.
• have a problem that causes muscle weakness (myasthenia gravis). Levofloxacin tablets should not be used in people who have a known history of myasthenia gravis.
• have a history of mental health problems, including depression.
• have central nervous system problems such as seizures (epilepsy).
• have nerve problems. Levofloxacin tablets should not be used in people who have a history of a nerve problem called peripheral neuropathy.
• have or anyone in your family has an irregular heartbeat, especially a condition called “QT prolongation.”
• have low blood potassium (hypokalemia).
• have bone problems.
• have joint problems including rheumatoid arthritis (RA).
• have kidney problems. You may need a lower dose of levofloxacin tablets if your kidneys do not work well.
• have liver problems.
• have diabetes or problems with low blood sugar (hypoglycemia).
• are pregnant or plan to become pregnant. It is not known if levofloxacin tablets will harm your unborn child.
• are breastfeeding or plan to breastfeed. Levofloxacin passes into your breast milk. You should not breastfeed during treatment with levofloxacin and for 2 days after taking your last dose of levofloxacin. You may pump your breast milk and throw it away during treatment with levofloxacin and for 2 days after taking your last dose of levofloxacin. If you are taking levofloxacin for inhalational anthrax, you and your healthcare provider should decide whether you can continue breastfeeding while taking levofloxacin.
Tell your healthcare provider about all the medicines you take, including prescription and over-the-counter medicines, vitamins, and herbal supplements.
Levofloxacin tablets and other medicines can affect each other causing side effects.
Especially tell your healthcare provider if you take:
• a steroid medicine.
• an anti-psychotic medicine.
• a tricyclic antidepressant.
• a water pill (diuretic).
• certain medicines may keep levofloxacin tablets from working correctly. Take levofloxacin tablets either 2 hours before or 2 hours after taking these medicines or supplements:
o an antacid, multivitamin, or other medicines or supplements that have magnesium, aluminum, iron, or zinc
o sucralfate (Carafate®)
o didanosine (Videx®, Videx® EC)
• a blood thinner (warfarin, Coumadin, Jantoven).
• an oral anti-diabetes medicine or insulin.
• an NSAID (Non-Steroidal Anti-Inflammatory Drug). Many common medicines for pain relief are NSAIDs. Taking an NSAID while you take levofloxacin tablets or other fluoroquinolones may increase your risk of central nervous system effects and seizures.
• theophylline (Theo-24®, Elixophyllin®, Theochron®, Uniphyl®, Theolair®).
• a medicine to control your heart rate or rhythm (antiarrhythmics).
Ask your healthcare provider if you are not sure if any of your medicines are listed above.
Know the medicines you take. Keep a list of your medicines and show it to your healthcare provider and pharmacist when you get a new medicine.

How should I take levofloxacin tablets?
• Take levofloxacin tablets exactly as your healthcare provider tells you to take it.
• Take levofloxacin tablets at the same time each day.
• Drink plenty of fluids while you take levofloxacin tablets.
• Levofloxacin tablets can be taken with or without food.
• If you miss a dose of levofloxacin tablets and it is:
o 8 hours or more until your next scheduled dose, take your missed dose right away. Then take the next dose at your regular time.
o less than 8 hours until your next scheduled dose, do not take the missed dose. Take the next dose at your regular time.
• Do not skip any doses of levofloxacin tablets or stop taking it, even if you begin to feel better, until you finish your prescribed treatment unless:
o you have tendon problems. See “What is the most important information I should know about levofloxacin tablets?”.
o you have a nerve problem. See “What is the most important information I should know about levofloxacin tablets?”.
o you have a central nervous system problem. See “What is the most important information I should know about levofloxacin tablets?”.
o you have a serious allergic reaction. See “What are the possible side effects of levofloxacin tablets?”.
o your healthcare provider tells you to stop taking levofloxacin tablets.
Taking all of your levofloxacin tablets doses will help make sure that all of the bacteria are killed. Taking all of your levofloxacin tablets doses will help you lower the chance that the bacteria will become resistant to levofloxacin. If your infection does not get better while you take levofloxacin tablets, it may mean that the bacteria causing your infection may be resistant to levofloxacin tablets. If your infection does not get better, call your healthcare provider. If your infection does not get better, levofloxacin tablets and other similar antibiotic medicines may not work for you in the future.
• If you take too much levofloxacin, call your healthcare provider or get medical help right away.

What should I avoid while taking levofloxacin tablets?
• Levofloxacin tablets can make you feel dizzy and lightheaded. Do notdrive, operate machinery, or do other activities that require mental alertness or coordination until you know how levofloxacin tablets affects you.
• Avoid sunlamps, tanning beds, and try to limit your time in the sun. Levofloxacin tablets can make your skin sensitive to the sun (photosensitivity) and the light from sunlamps and tanning beds. You could get severe sunburn, blisters or swelling of your skin. If you get any of these symptoms while you take levofloxacin tablets, call your healthcare provider right away. You should use sunscreen and wear a hat and clothes that cover your skin if you have to be in sunlight.

What are the possible side effects of levofloxacin tablets?
Levofloxacin tablets may cause serious side effects, including:
• See “What is the most important information I should know about levofloxacin tablets?”
• Serious allergic reactions. Allergic reactions can happen in people taking fluoroquinolones, including levofloxacin tablets, even after only 1 dose. Stop taking levofloxacin tablets and get emergency medical help right away if you have any of the following symptoms of a severe allergic reaction:
o hives
o trouble breathing or swallowing
o swelling of the lips, tongue, face
o throat tightness, hoarseness
o rapid heartbeat
o faint
o skin rash
Skin rash may happen in people taking levofloxacin tablets, even after only 1 dose. Stop taking levofloxacin tablets at the first sign of a skin rash and immediately call your healthcare provider. Skin rash may be a sign of a more serious reaction to levofloxacin tablets.
• Liver damage (hepatotoxicity): Hepatotoxicity can happen in people who take levofloxacin tablets. Call your healthcare provider right away if you have unexplained symptoms such as:
o nausea or vomiting
o stomach pain
o fever
o weakness
o pain or tenderness in the upper right side of your stomach-area
o itching
o unusual tiredness
o loss of appetite
o light colored bowel movements
o dark colored urine
o yellowing of your skin or the whites of your eyes
Stop taking levofloxacin tablets and tell your healthcare provider right away if you have yellowing of your skin or white part of your eyes, or if you have dark urine. These can be signs of a serious reaction to levofloxacin tablets (a liver problem).
• Aortic aneurysm and dissection: Tell your healthcare provider if you have ever been told that you have an aortic aneurysm, a swelling of the large artery that carries blood from the heart to the body. Get emergency medical help right away if you have sudden chest, stomach, or back pain.
• Intestine infection (Clostridium difficile-associated diarrhea) . Clostridium difficile-associated diarrhea (CDAD) can happen with many antibiotics, including levofloxacin tablets. Call your healthcare provider right away if you get watery diarrhea, diarrhea that does not go away, or bloody stools. You may have stomach cramps and a fever. CDAD can happen 2 or more months after you have finished your antibiotic.
• Serious heart rhythm changes (QT prolongation and torsades de pointes).
Tell your healthcare provider right away if you have a change in your heart beat (a fast or irregular heartbeat), or if you faint. Levofloxacin tablets may cause a rare heart problem known as prolongation of the QT interval. This condition can cause an abnormal heartbeat and can be very dangerous. The chances of this happening are higher in people:
o who are elderly
o with a family history of prolonged QT interval
o with low blood potassium (hypokalemia)
o who take certain medicines to control heart rhythm (antiarrhythmics)
• Joint Problems. Increased chance of problems with joints and tissues around joints in children can happen. Tell your child’s healthcare provider if your child has any joint problems during or after treatment with levofloxacin tablets.
• Changes in blood sugar. People who take levofloxacin tablets and other fluoroquinolone medicines with oral anti-diabetes medicines or with insulin can get low blood sugar (hypoglycemia) and high blood sugar (hyperglycemia). Follow your healthcare provider’s instructions for how often to check your blood sugar. If you have diabetes and you get low blood sugar while taking levofloxacin tablets, stop taking levofloxacin tablets and call your healthcare provider right away. Your antibiotic medicine may need to be changed.
• Sensitivity to sunlight (photosensitivity). See “What should I avoid while taking levofloxacin tablets?”
The most common side effects of levofloxacin tablets include:
o nausea
o headache
o diarrhea
o insomnia
o constipation
o dizziness
In children 6 months and older who take levofloxacin tablets to treat anthrax disease or plague, vomiting is also common.
Levofloxacin tablets may cause false-positive urine screening results for opiates when testing is done with some commercially available kits. A positive result should be confirmed using a more specific test.
These are not all the possible side effects of levofloxacin tablets.
Call your doctor for medical advice about side effects. You may report side effects to FDA at 1-800-FDA-1088.

How should I store levofloxacin tablets?
• Store levofloxacin tablets at 20° to 25°C (68° to 77°F)
• Keep levofloxacin tablets in a tightly closed container.

General information about the safe and effective use of levofloxacin tablets.
Medicines are sometimes prescribed for purposes other than those listed in a Medication Guide. Do not use levofloxacin tablets for a condition for which it is not prescribed. Do not give levofloxacin tablets to other people, even if they have the same symptoms that you have. They may harm them.
This Medication Guide summarizes the most important information about levofloxacin tablets. If you would like more information about levofloxacin tablets, talk with your healthcare provider. You can ask your healthcare provider or pharmacist for information about levofloxacin tablets that is written for healthcare professionals.

What are the ingredients in levofloxacin tablets?
Active ingredient: levofloxacin, USP
Inactive ingredients: croscarmellose sodium, hypromellose, magnesium stearate, microcrystalline cellulose, polyethylene glycol, polysorbate 80, povidone and titanium dioxide.
Levofloxacin tablets USP, 250 mg also contains iron oxide red.
Levofloxacin tablets USP, 500 mg also contains iron oxide red and iron oxide yellow.
The brands listed are trademarks of their respective owners and are not trademarks of Hetero Labs Limited.

This Medication Guide has been approved by the U.S. Food and Drug Administration.

Revised: 07/2024

Repackaged By / Distributed By: RemedyRepack Inc.

625 Kolter Drive, Indiana, PA 15701

(724) 465-8762

PACKAGE LABEL

DRUG: Levofloxacin

GENERIC: Levofloxacin

DOSAGE: TABLET, FILM COATED

ADMINSTRATION: ORAL

NDC: 70518-0968-0

NDC: 70518-0968-1

NDC: 70518-0968-2

NDC: 70518-0968-3

COLOR: white

SHAPE: CAPSULE

SCORE: No score

SIZE: 21 mm

IMPRINT: I;18

PACKAGING: 30 in 1 BLISTER PACK

PACKAGING: 20 in 1 BLISTER PACK

PACKAGING: 7 in 1 BOTTLE PLASTIC

PACKAGING: 5 in 1 BOTTLE PLASTIC

ACTIVE INGREDIENT(S):

- LEVOFLOXACIN 750mg in 1

INACTIVE INGREDIENT(S):

- CROSCARMELLOSE SODIUM
- HYPROMELLOSES
- MAGNESIUM STEARATE
- CELLULOSE, MICROCRYSTALLINE
- POLYETHYLENE GLYCOL, UNSPECIFIED
- POLYSORBATE 80
- POVIDONE
- TITANIUM DIOXIDE